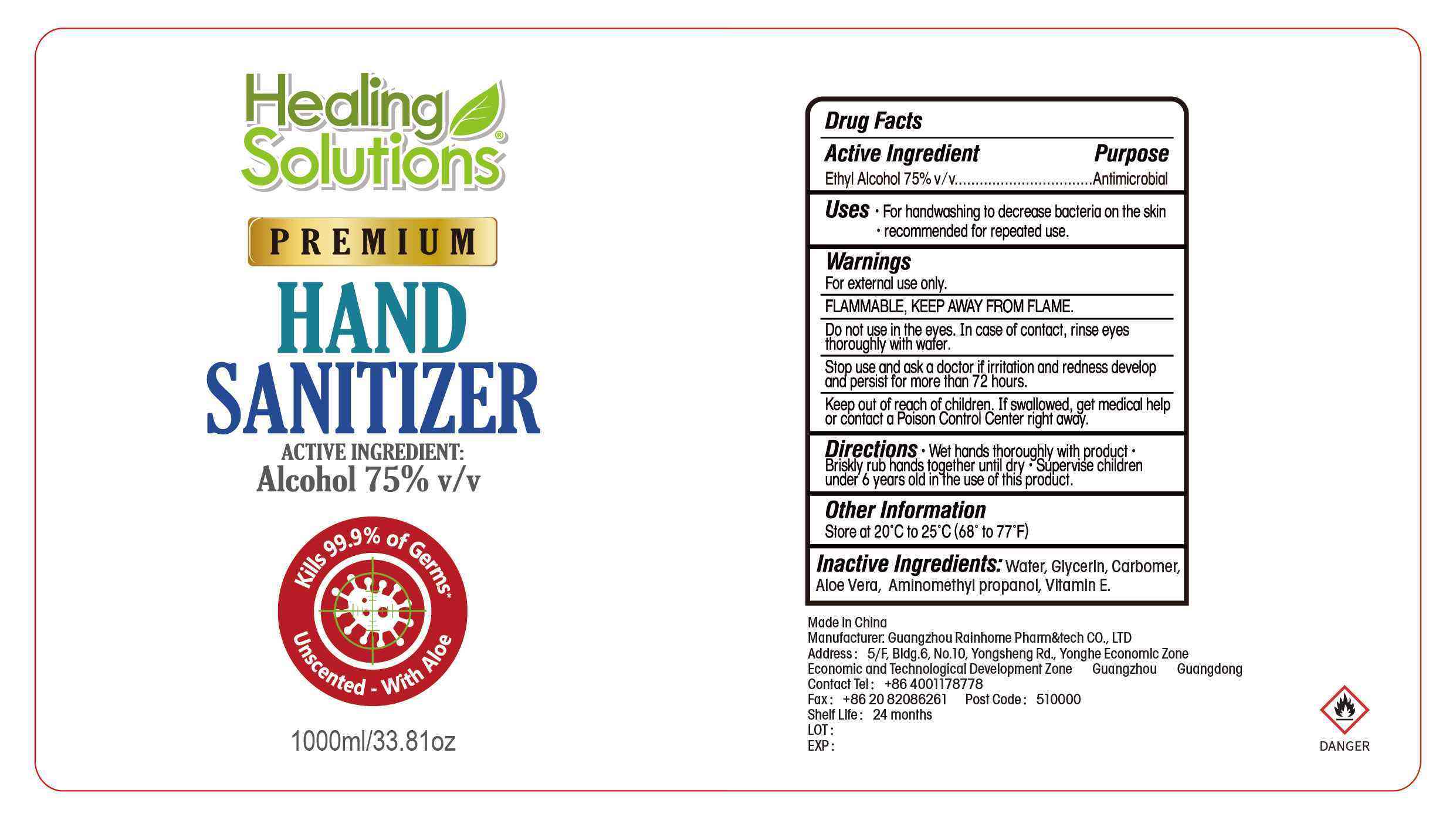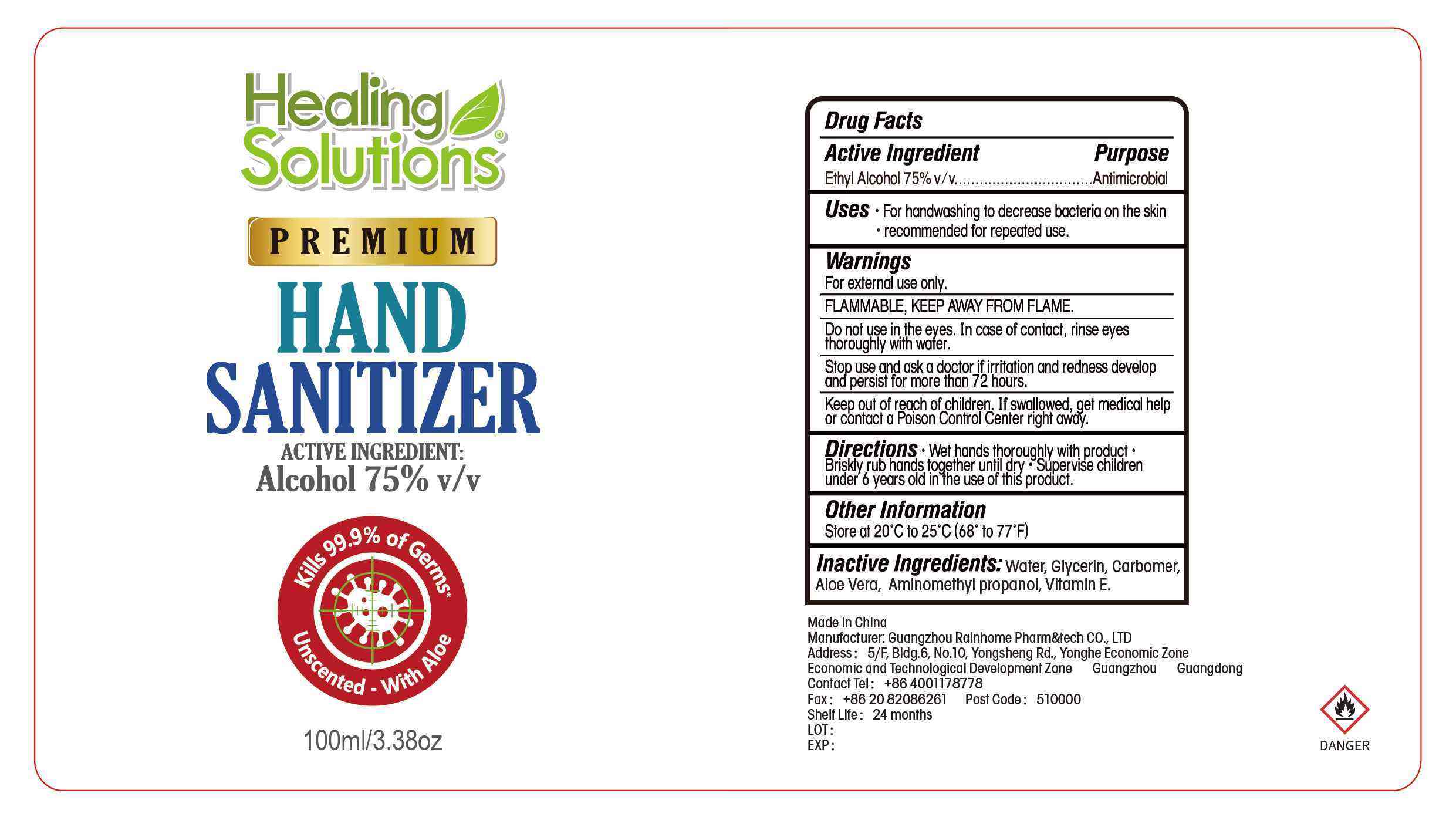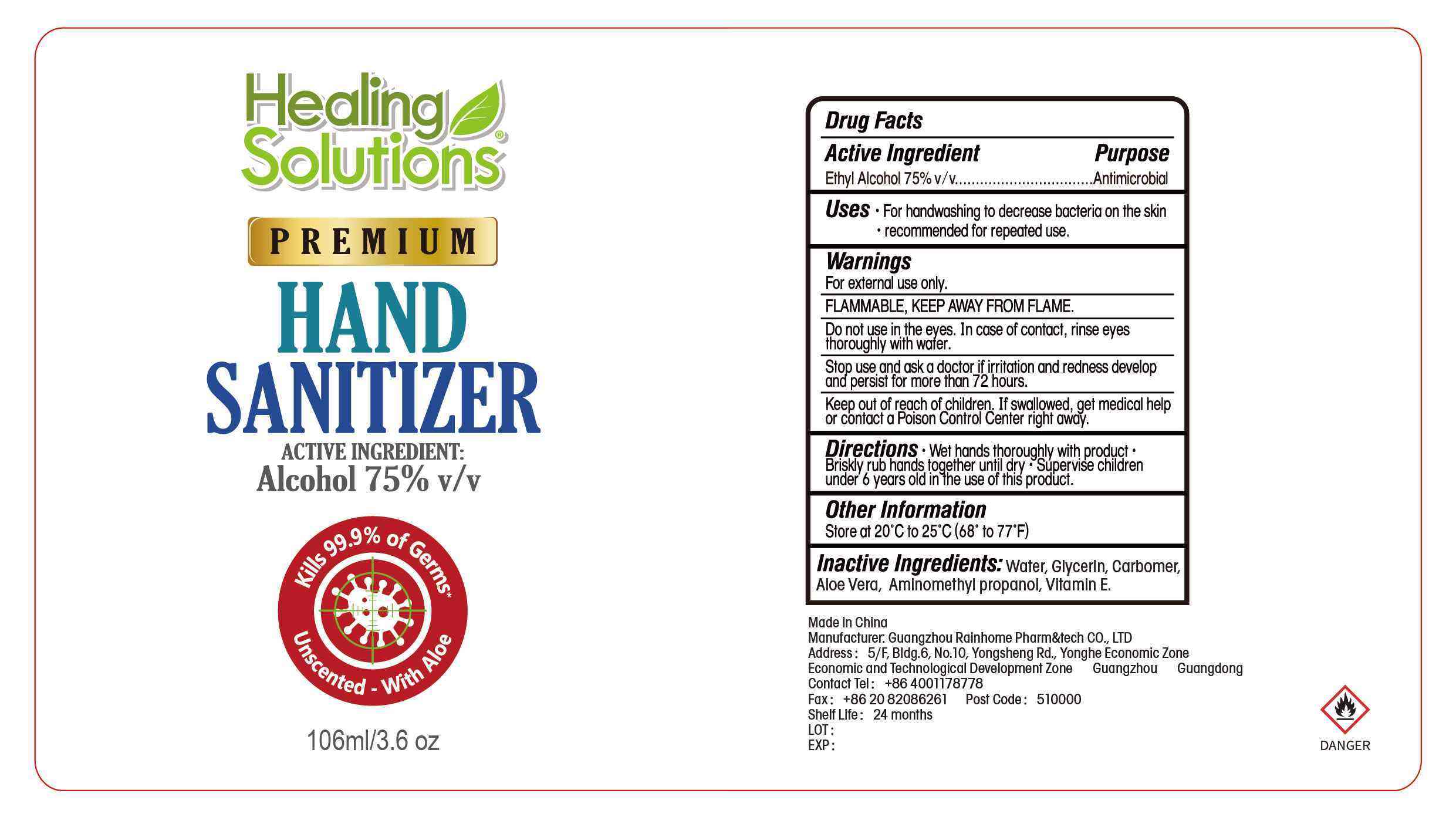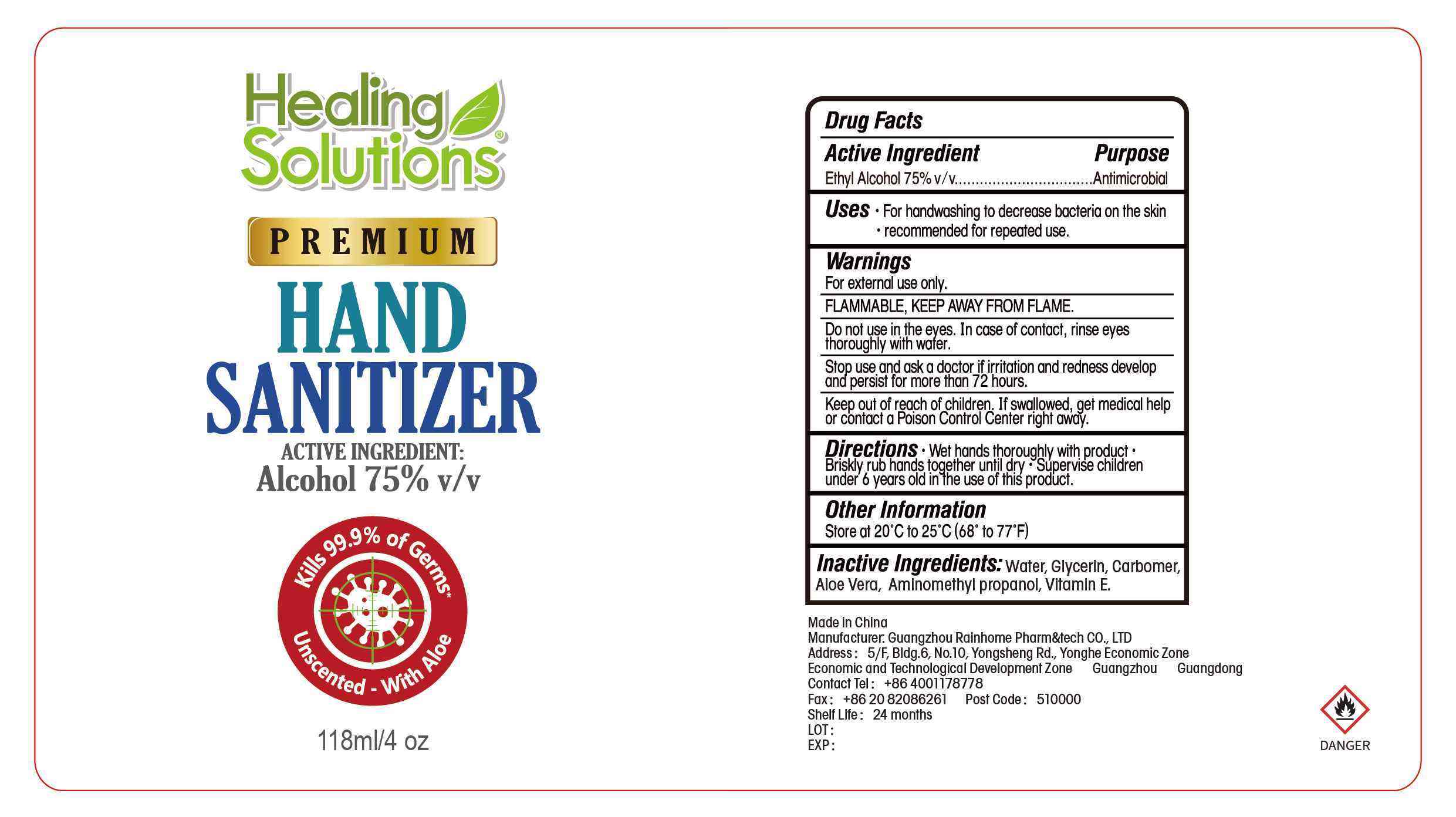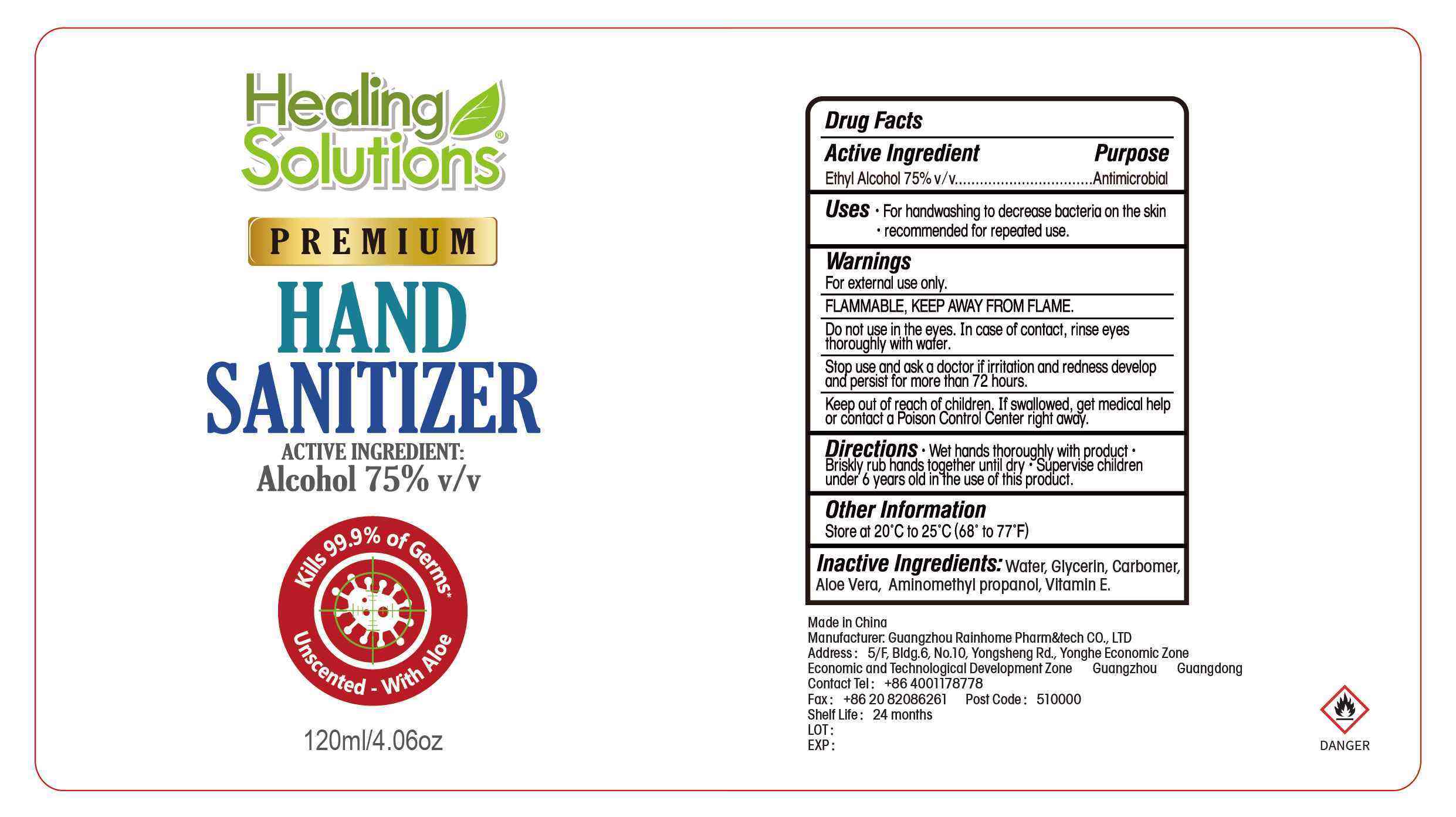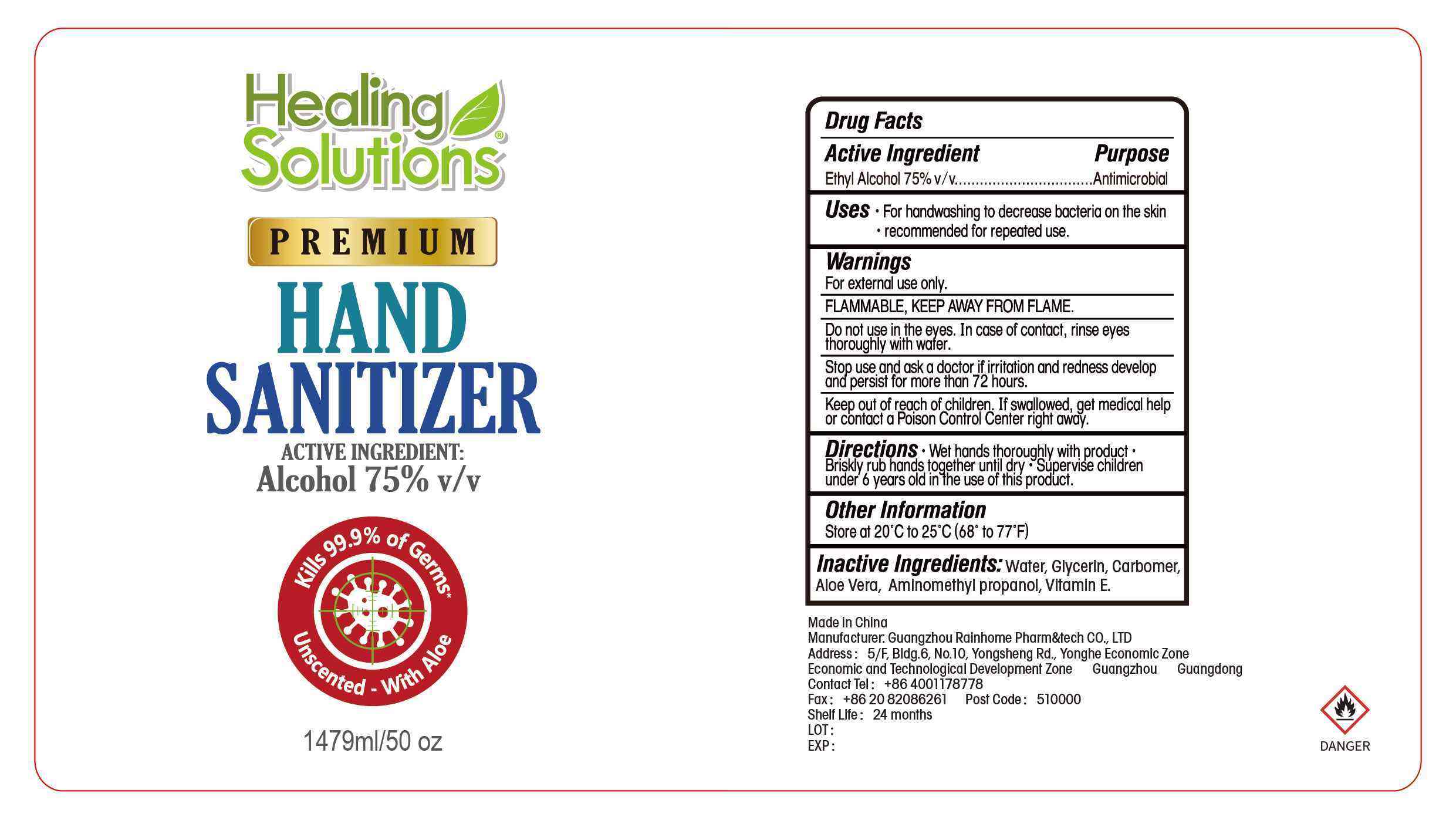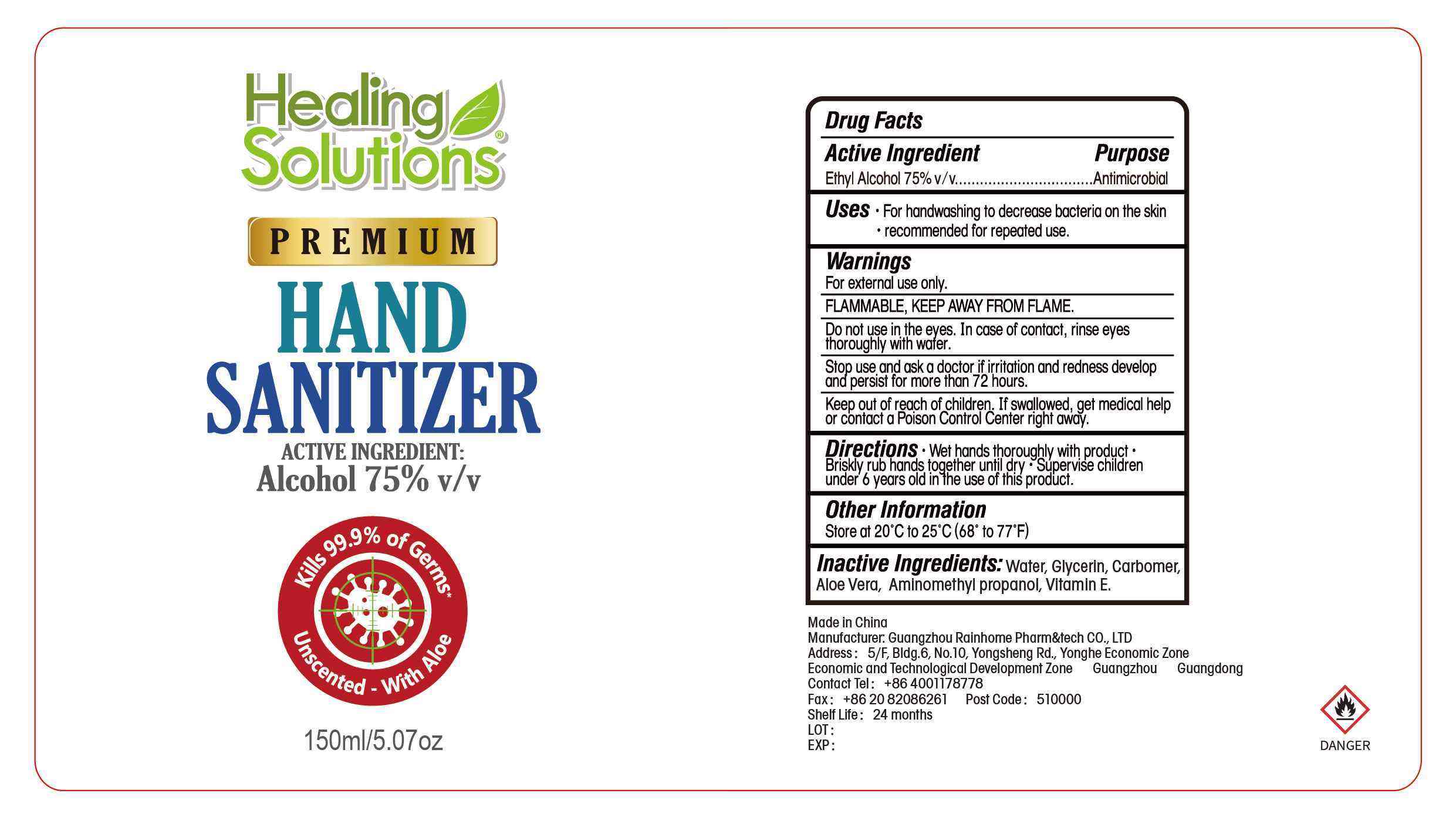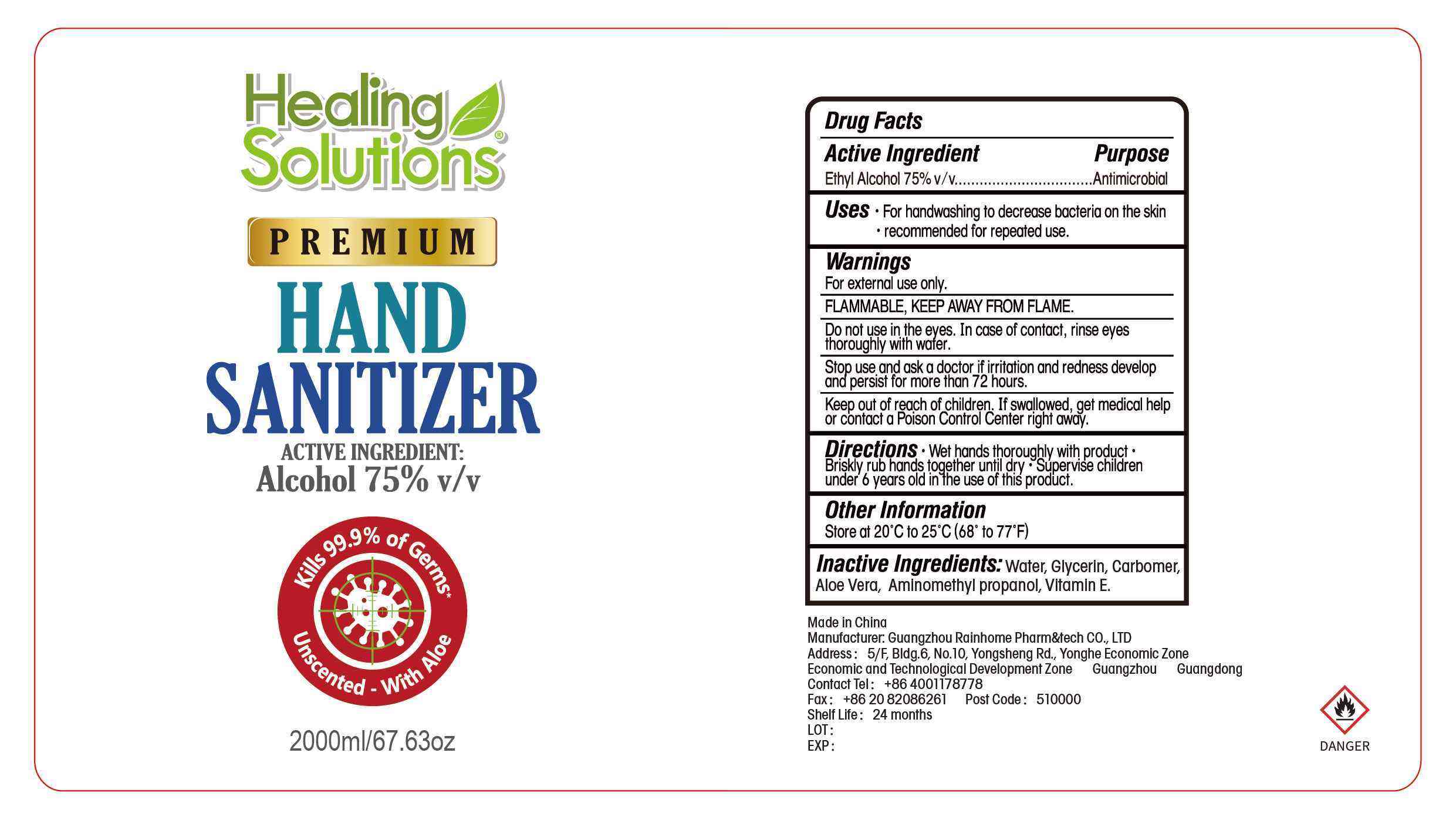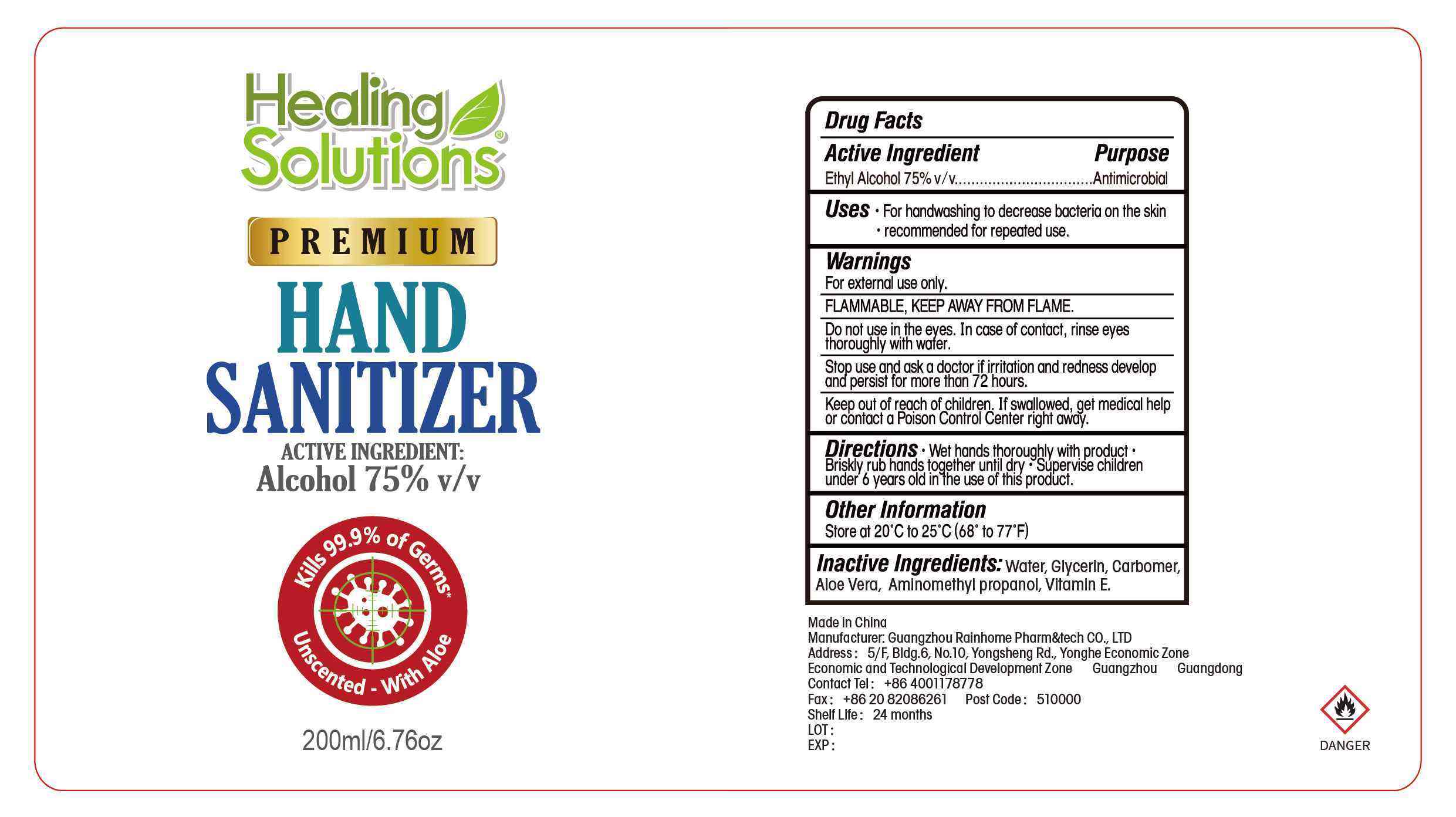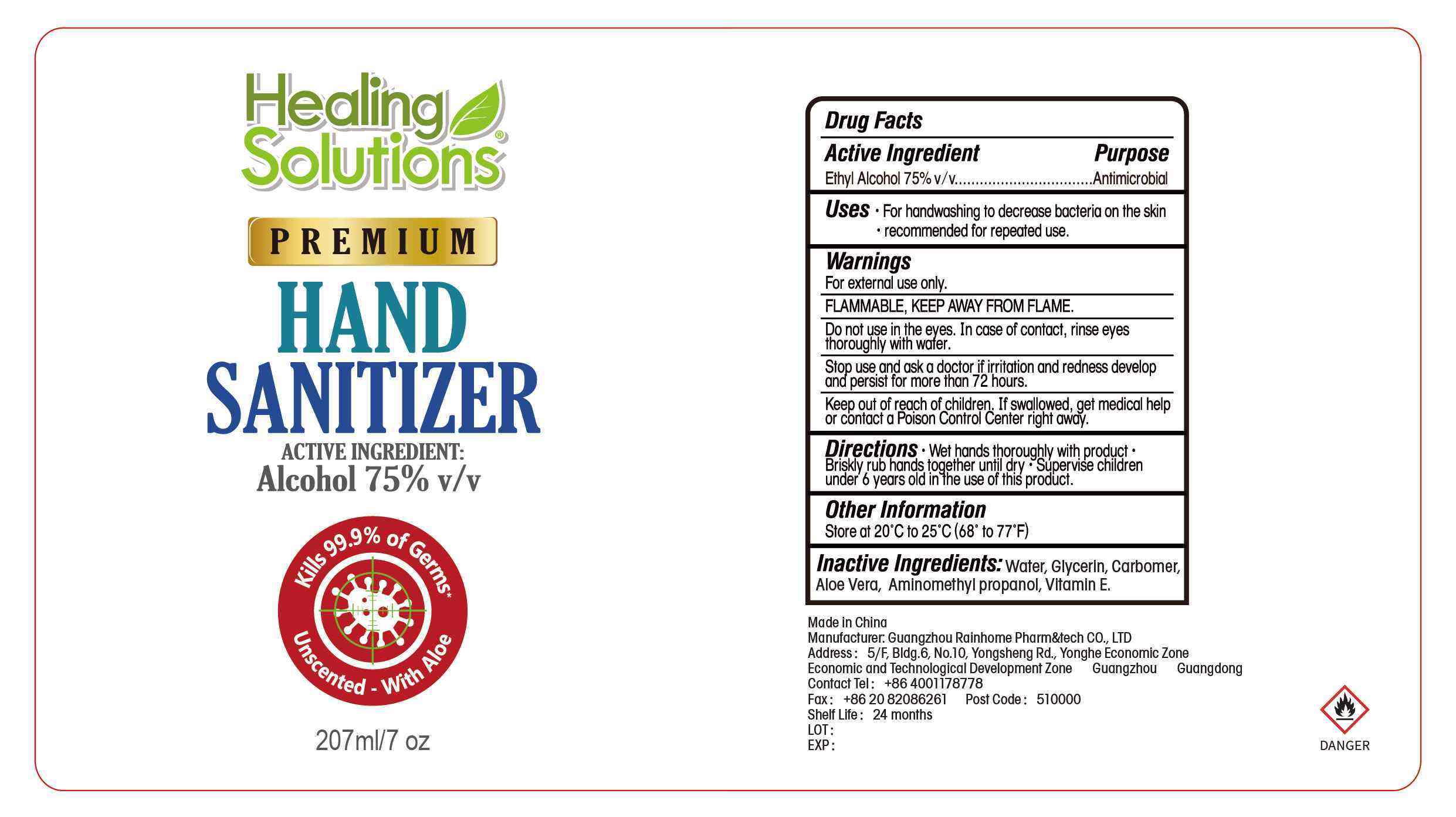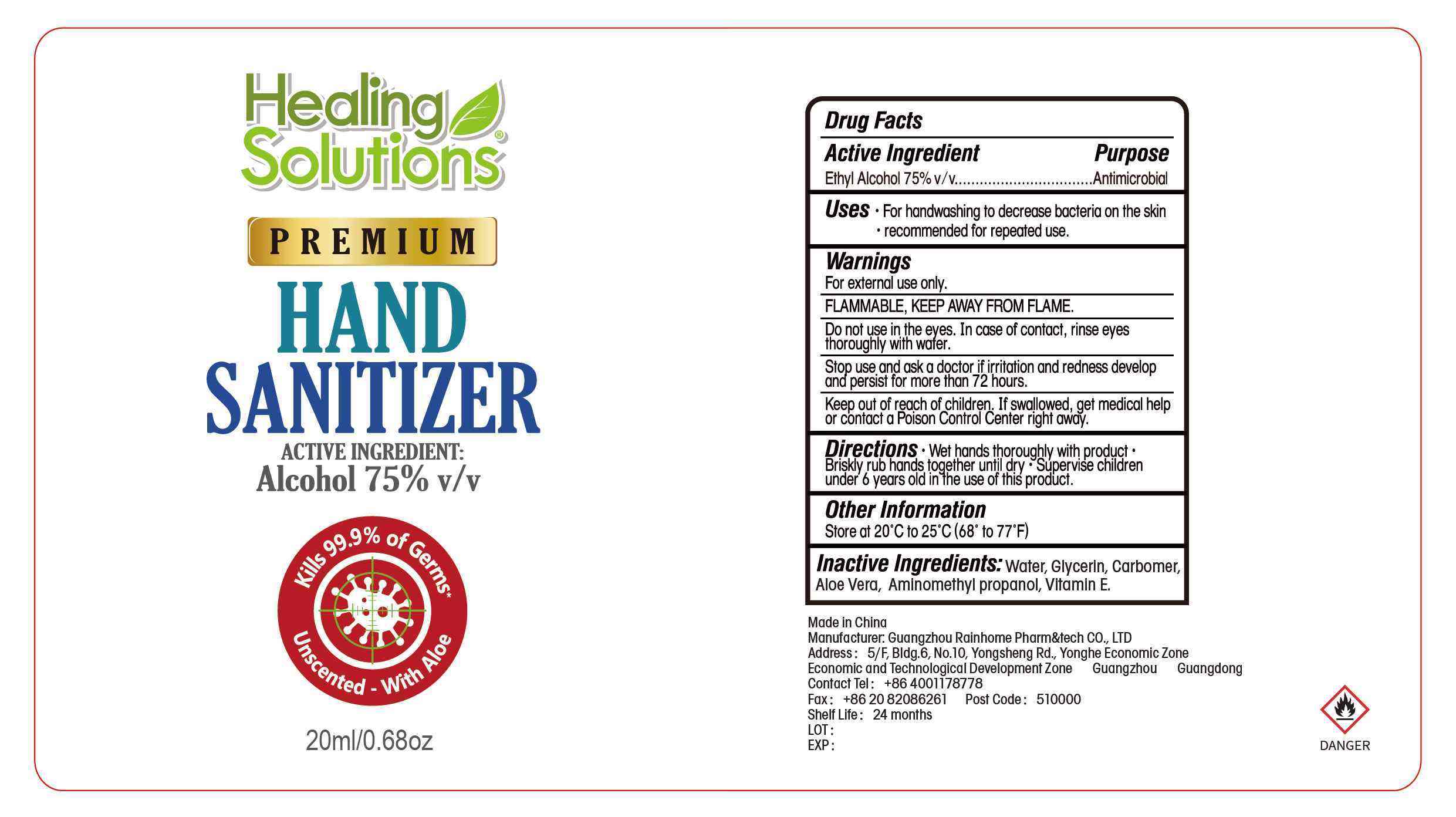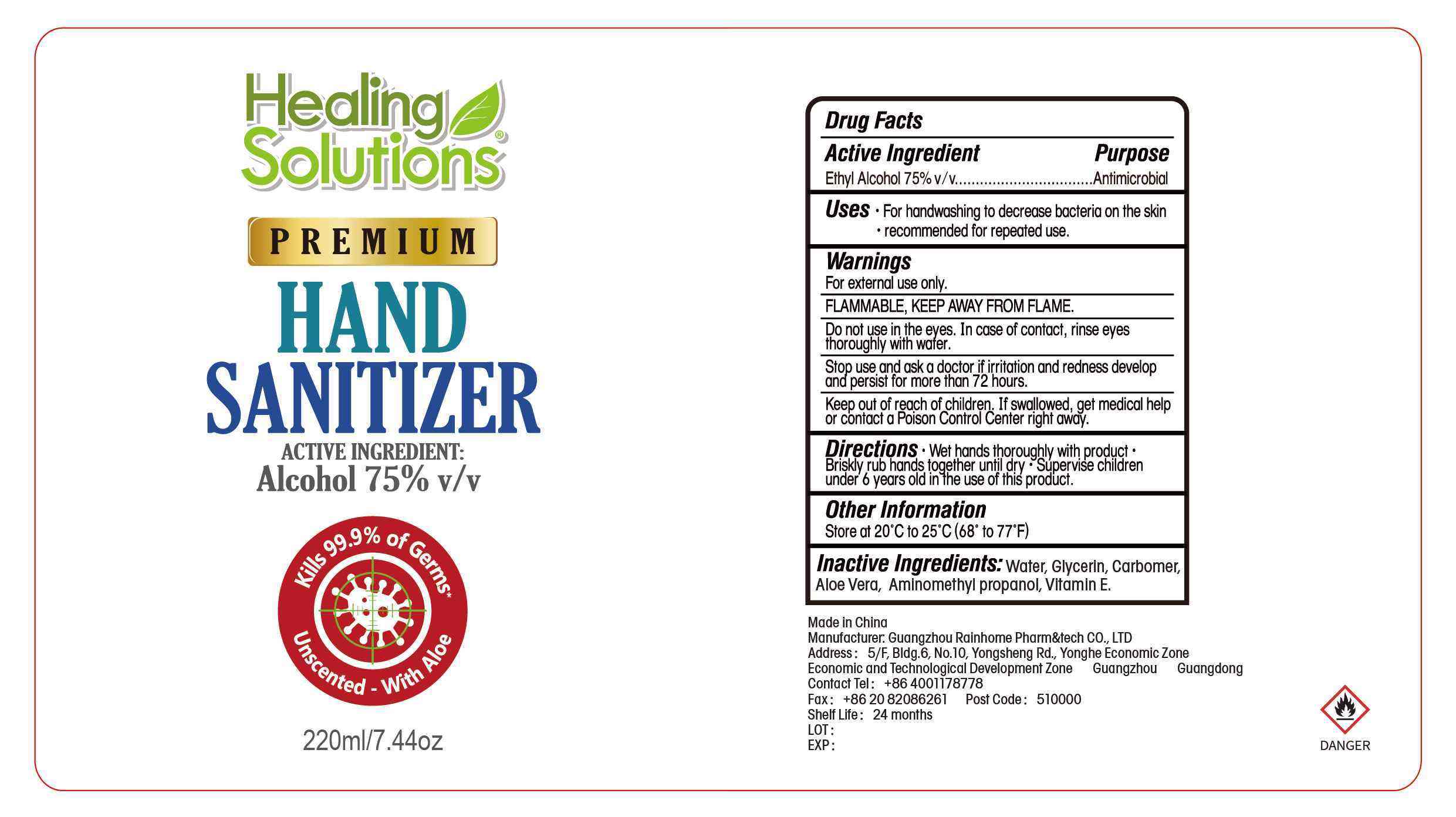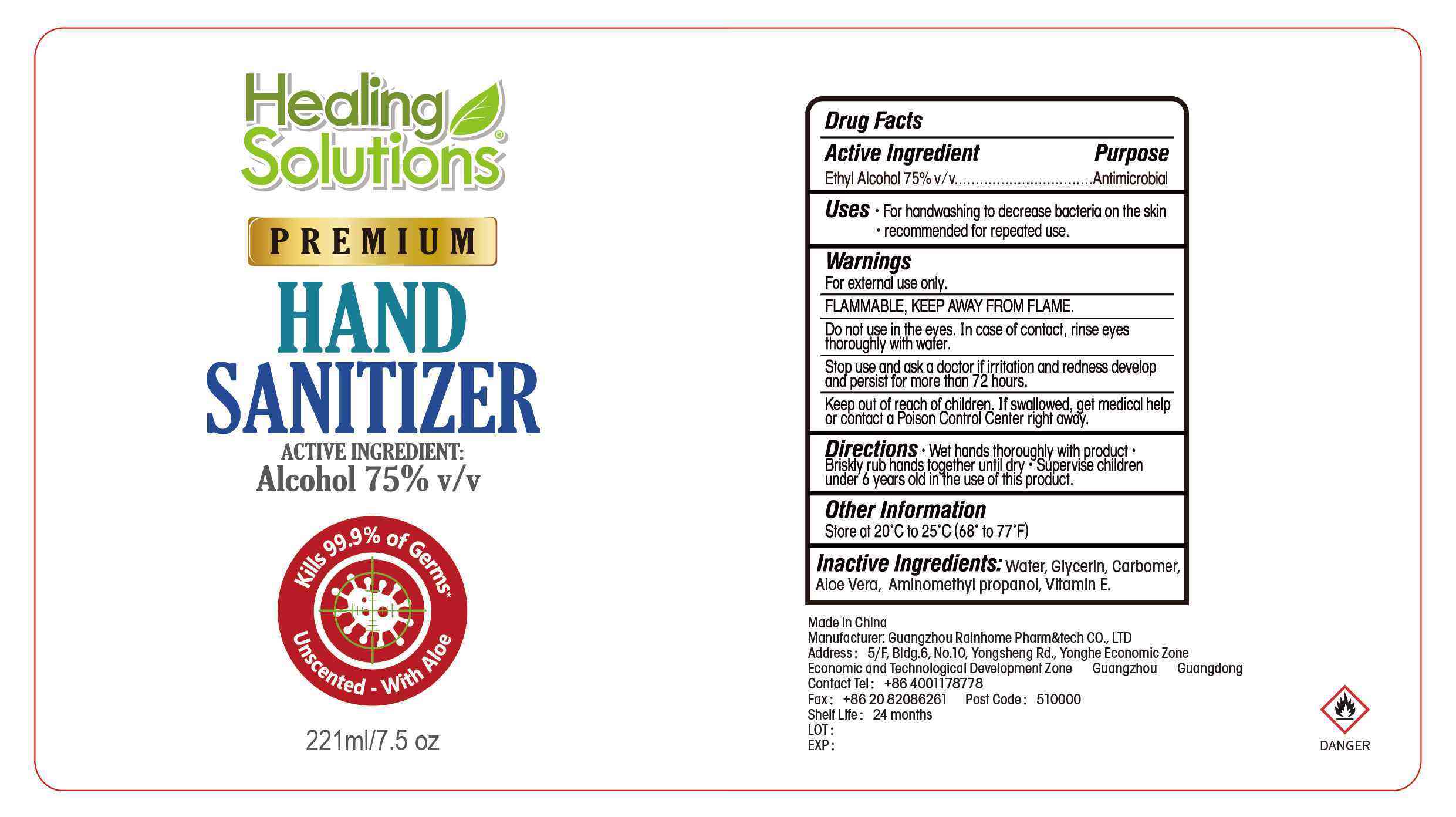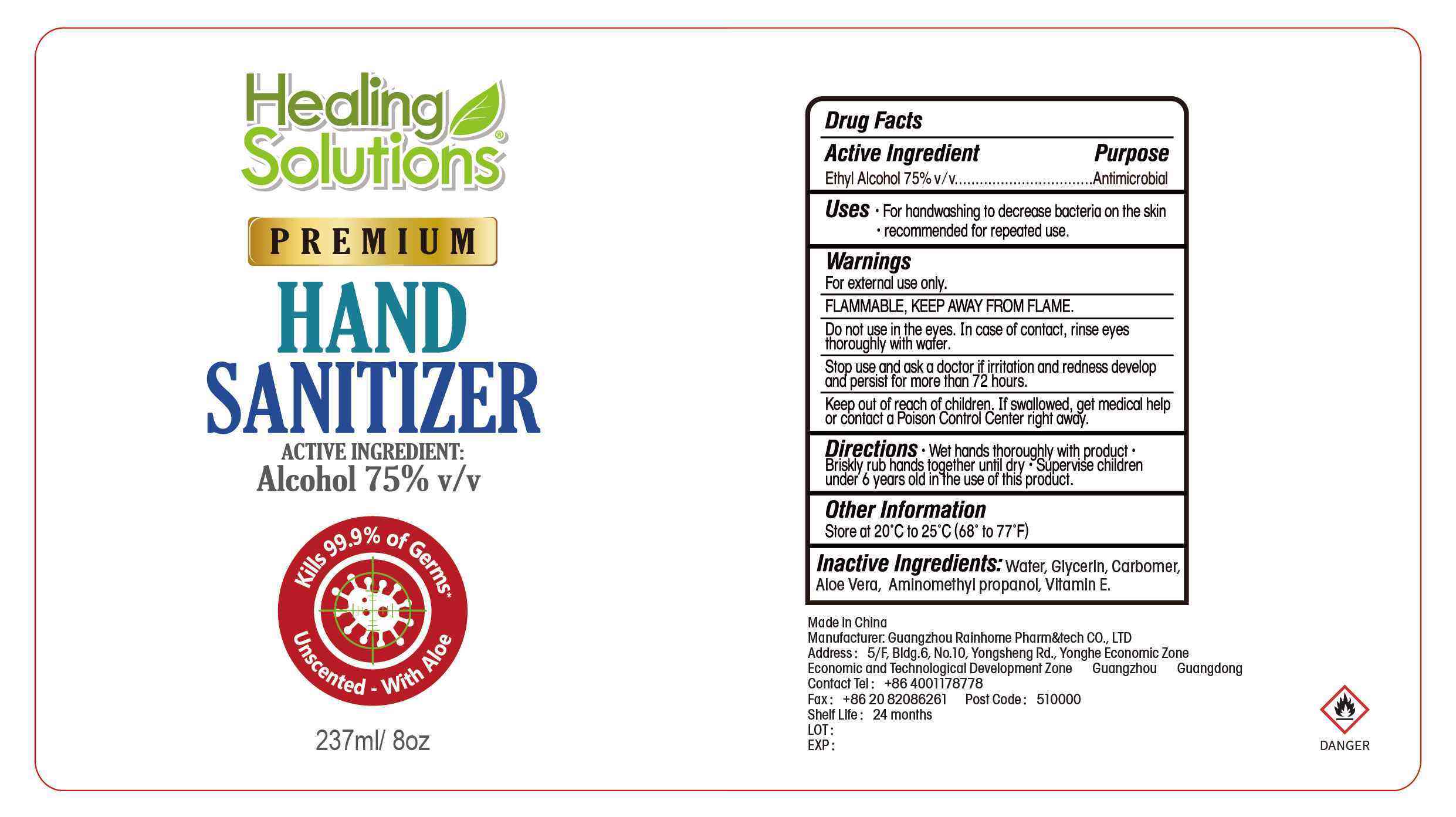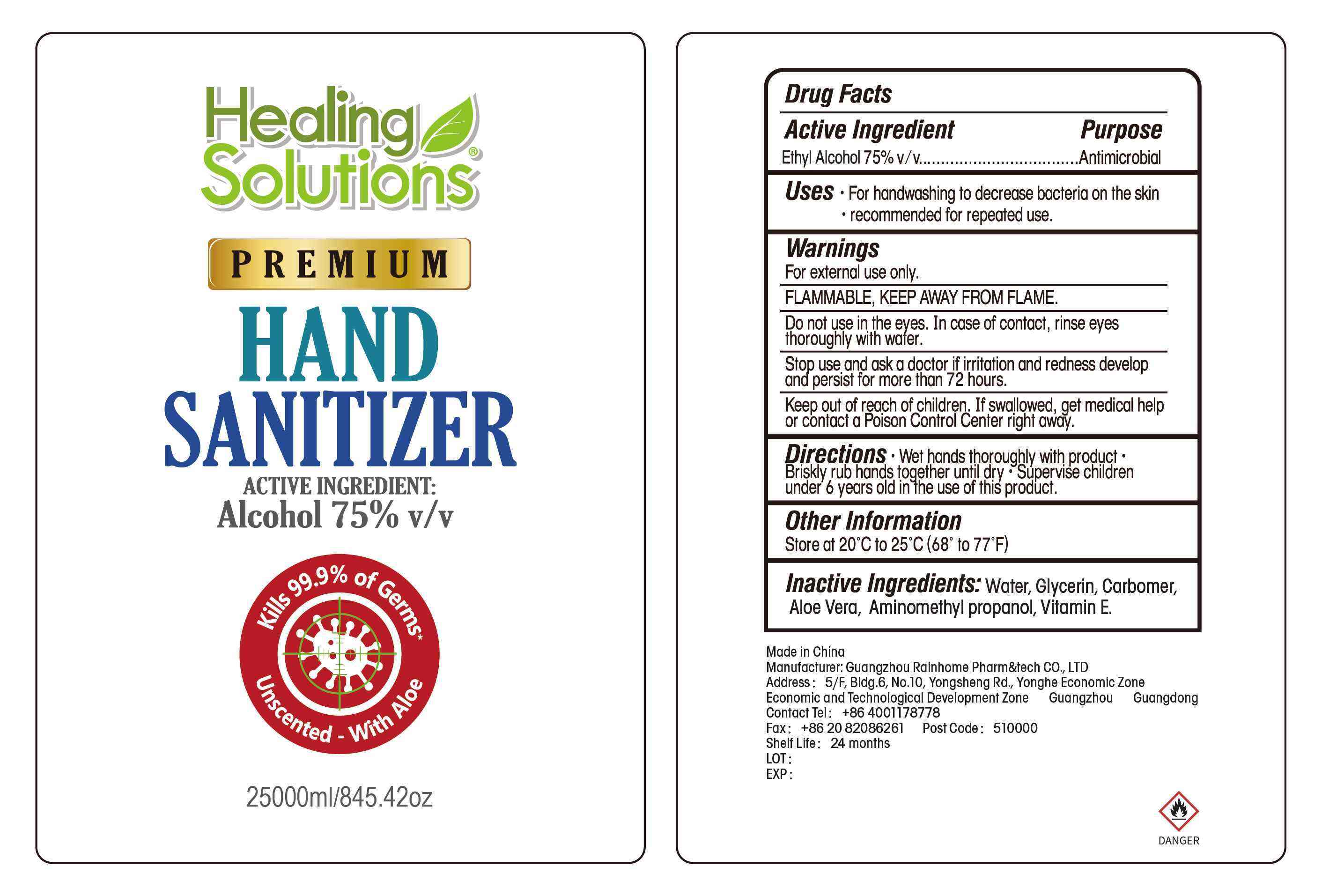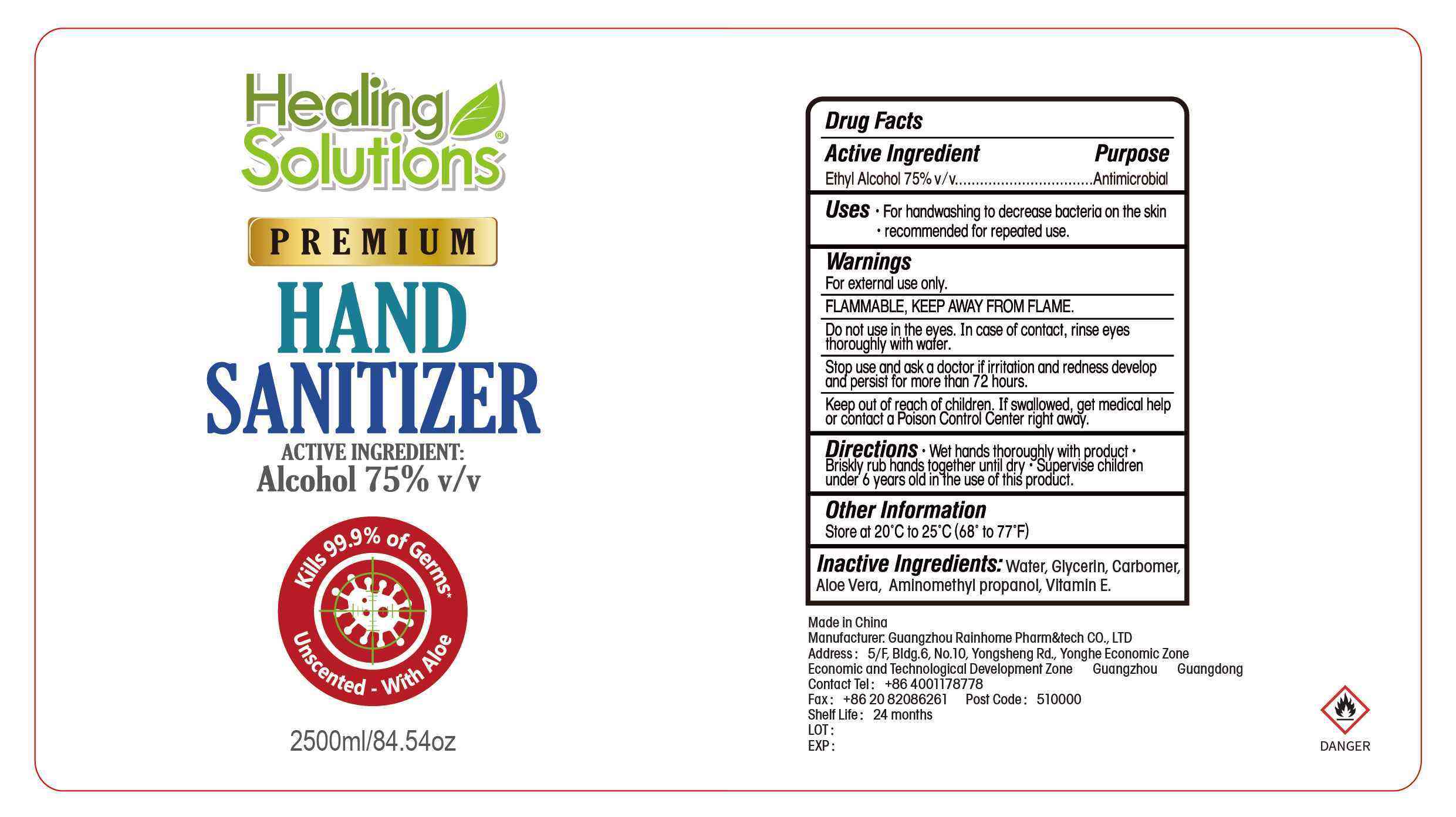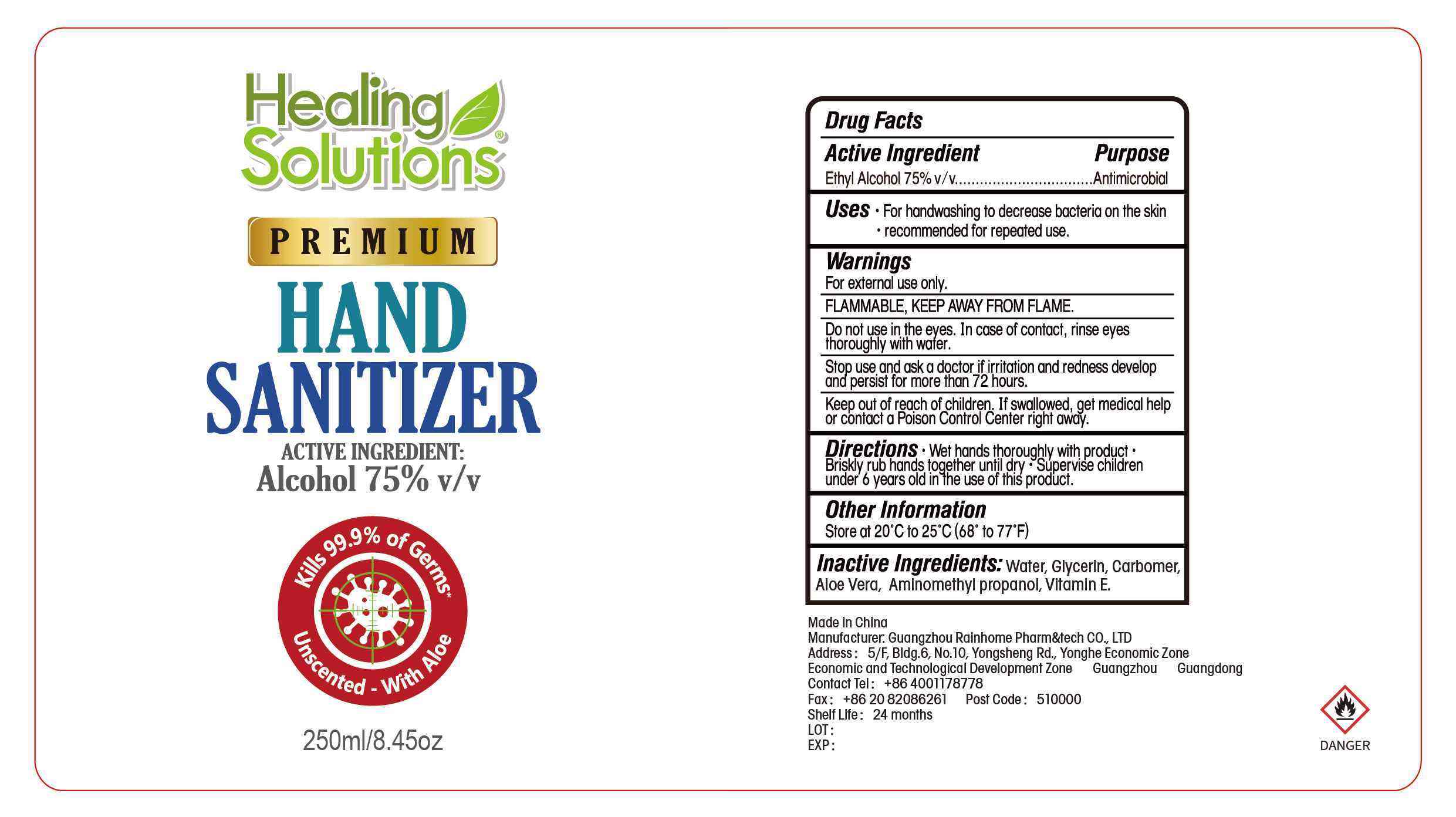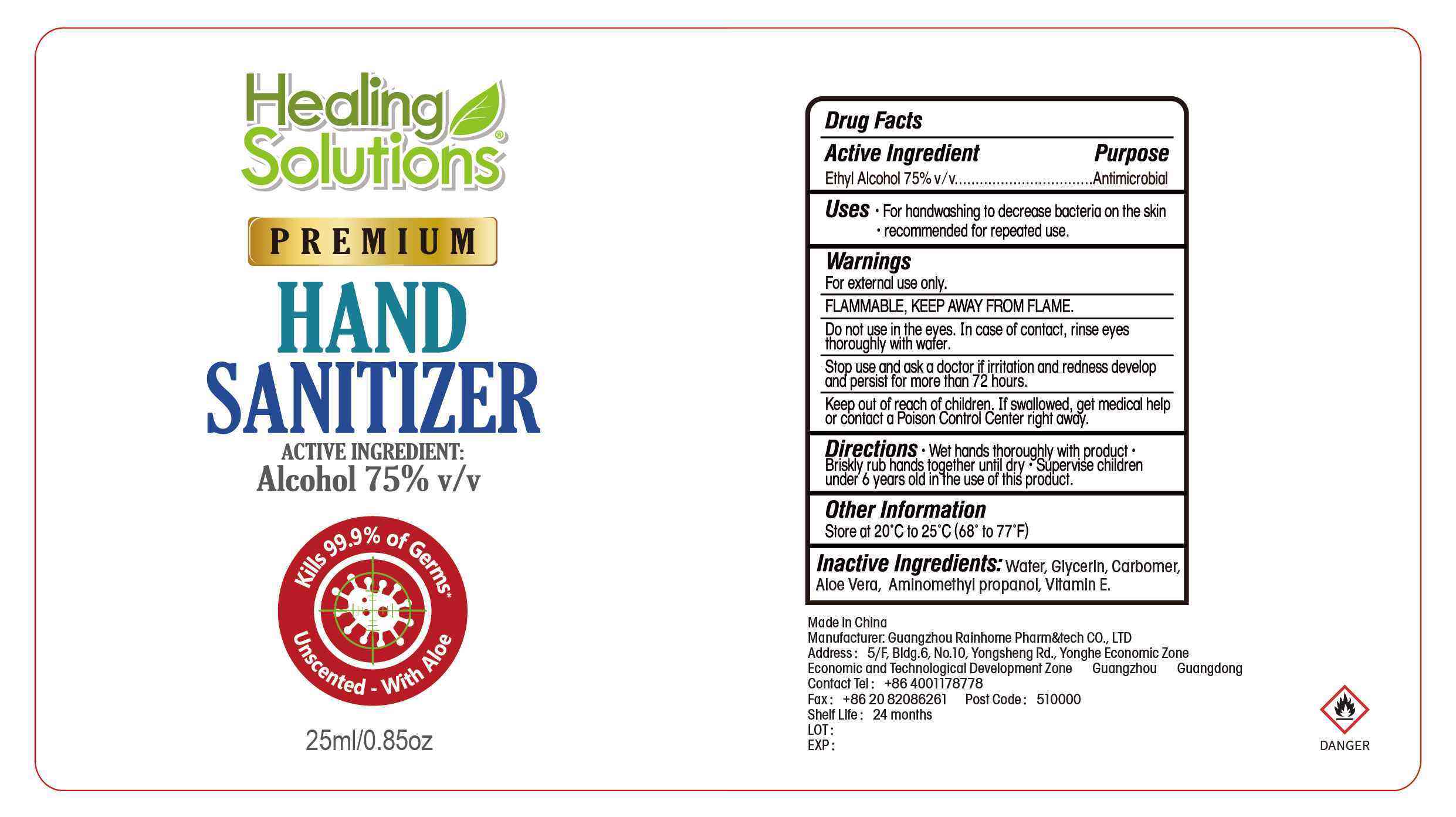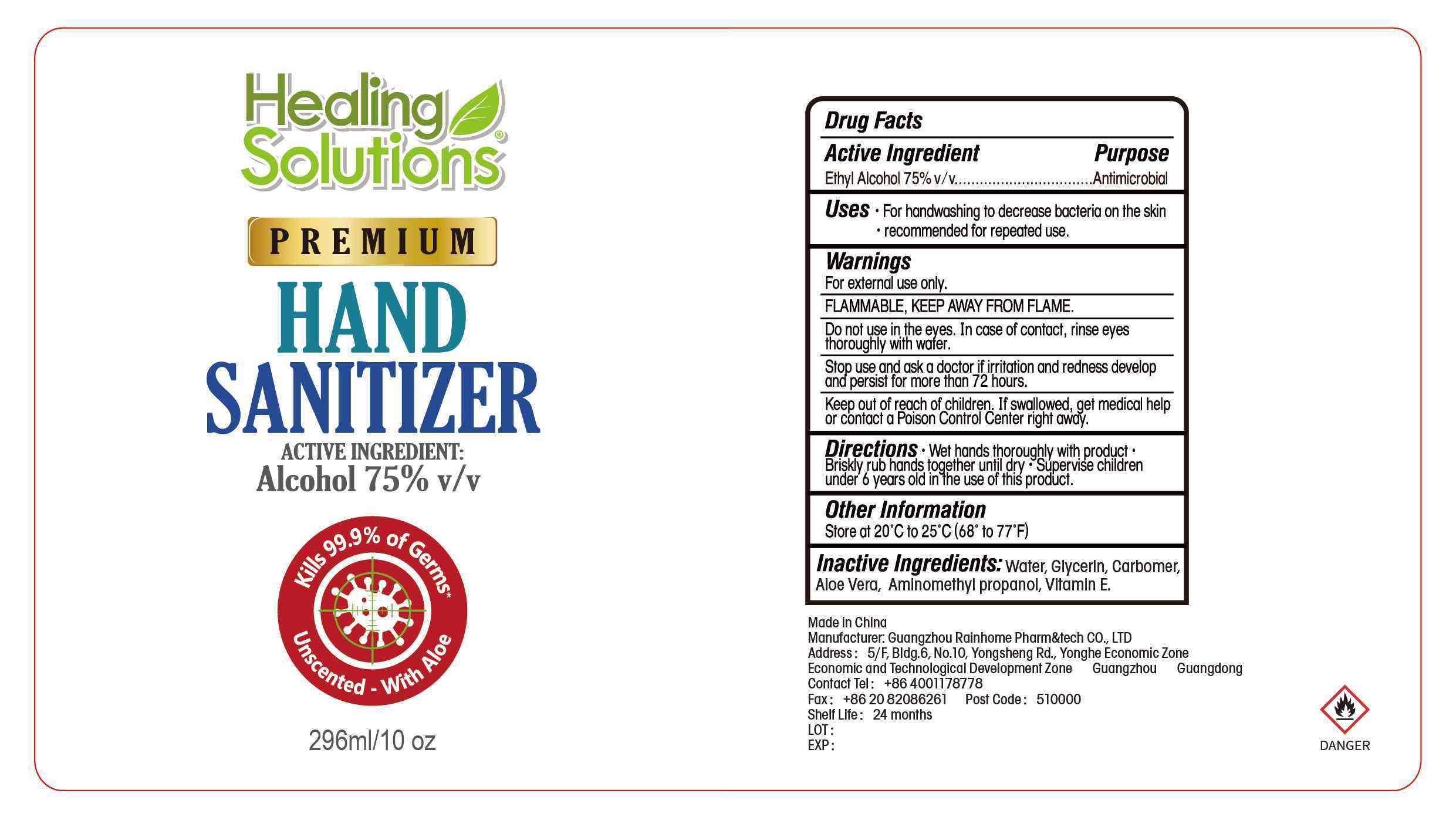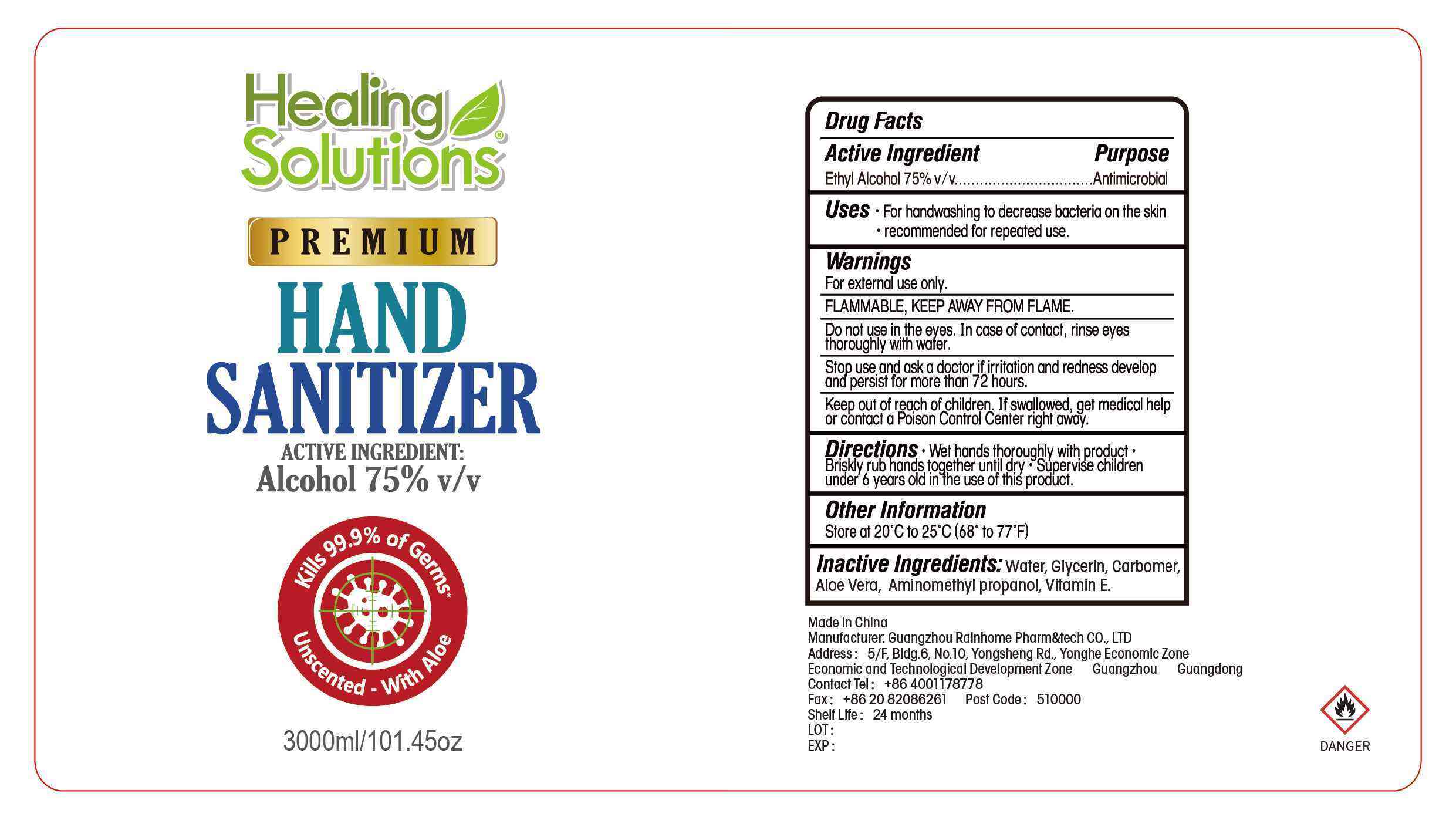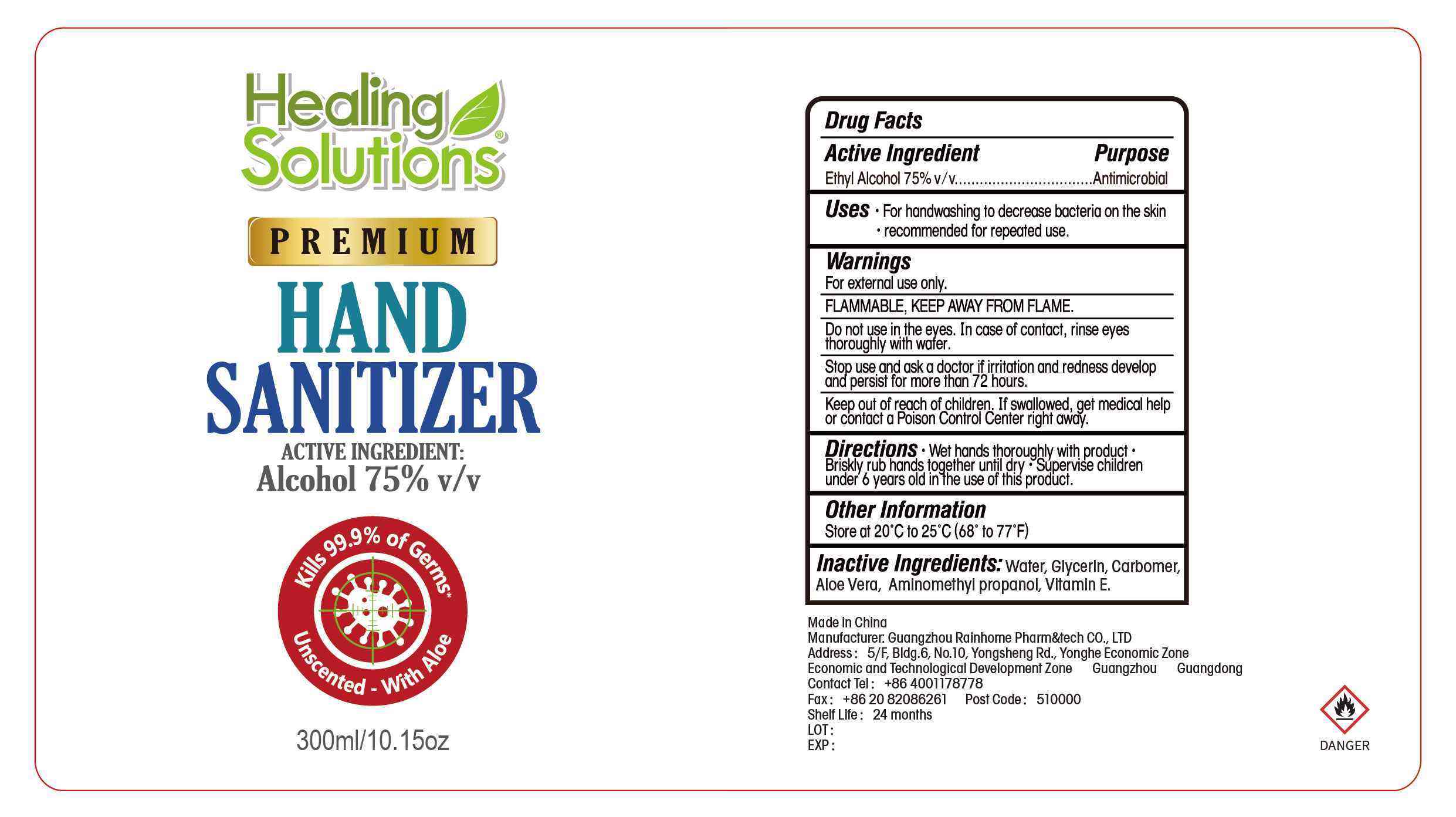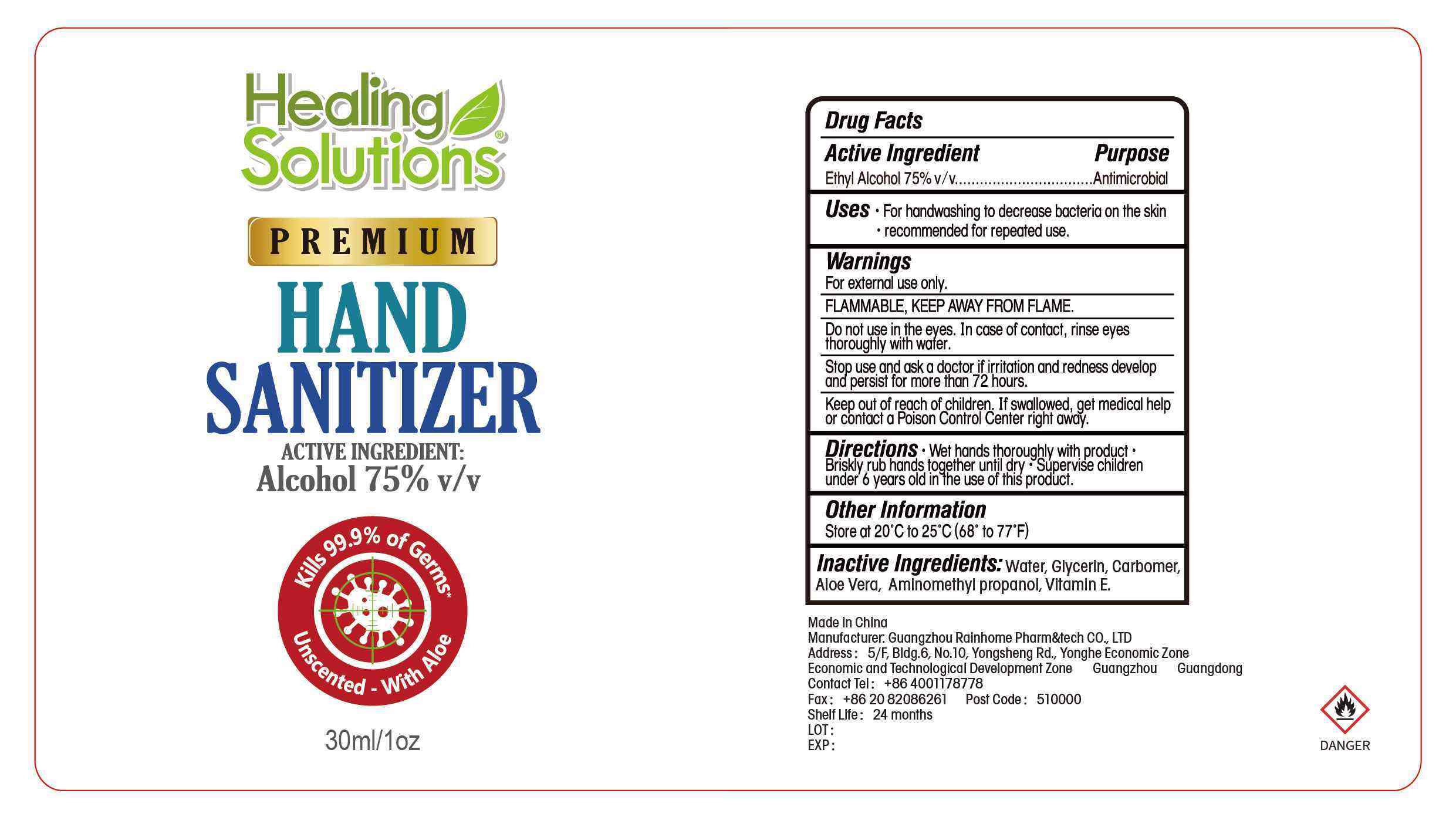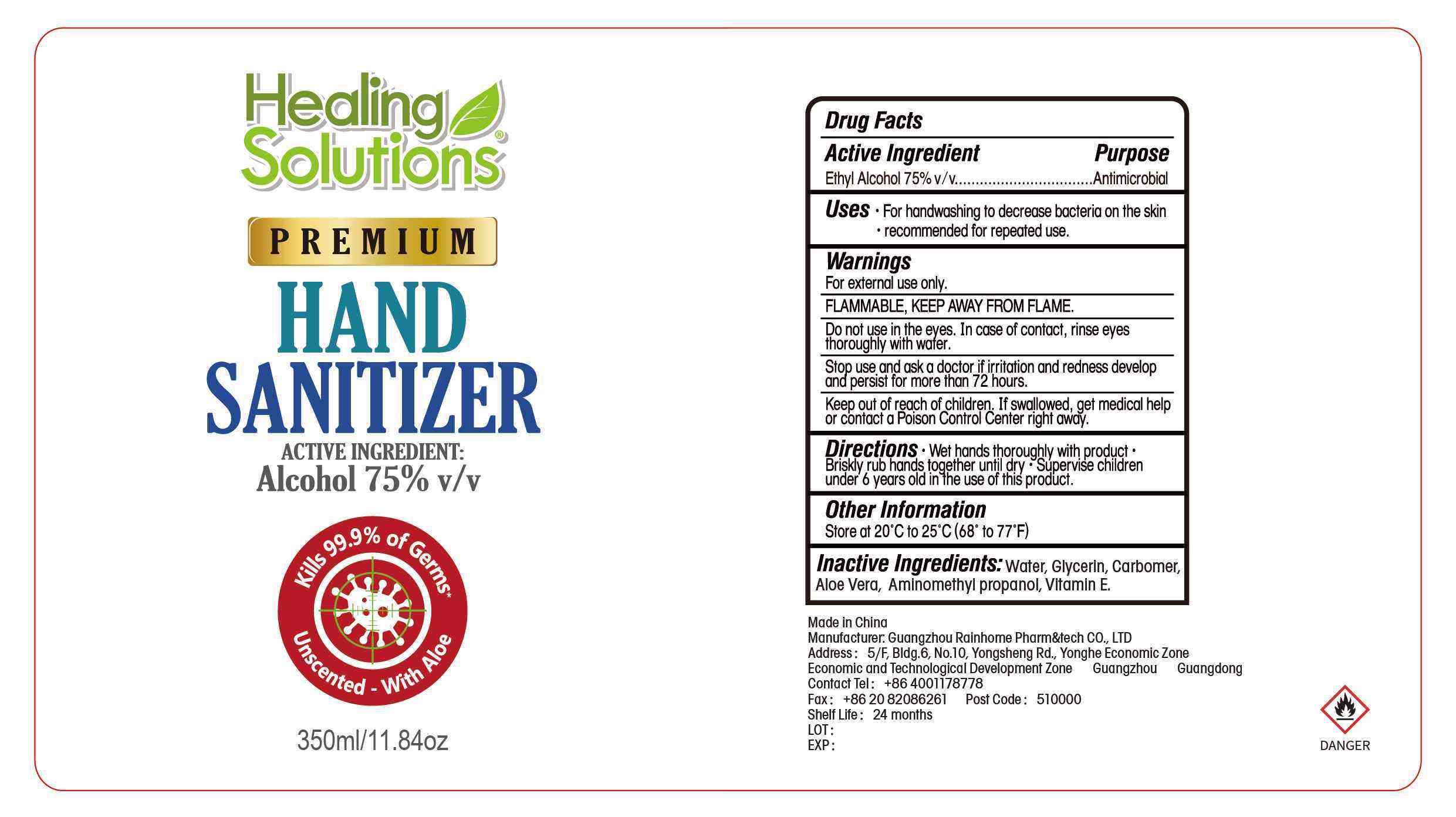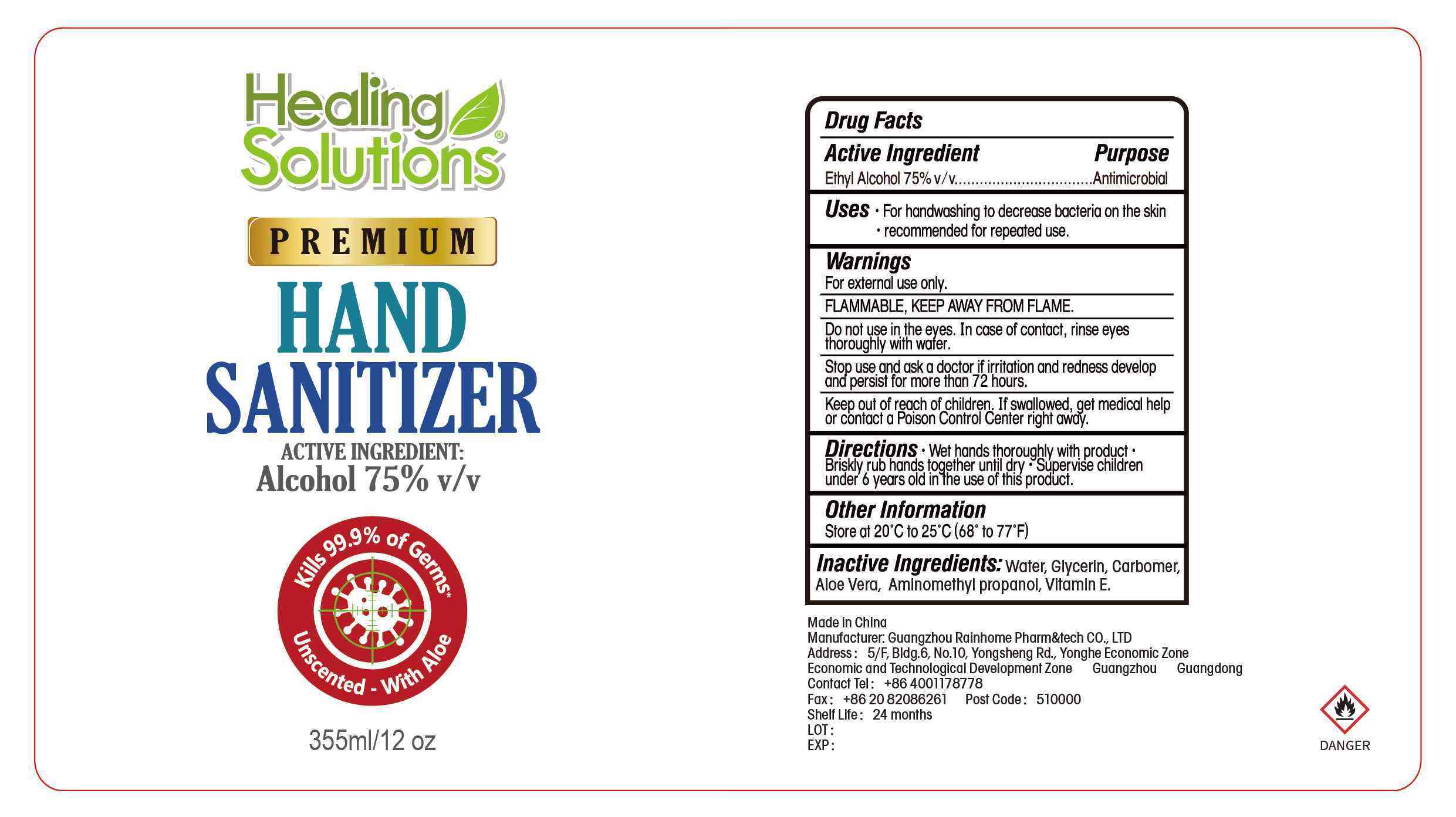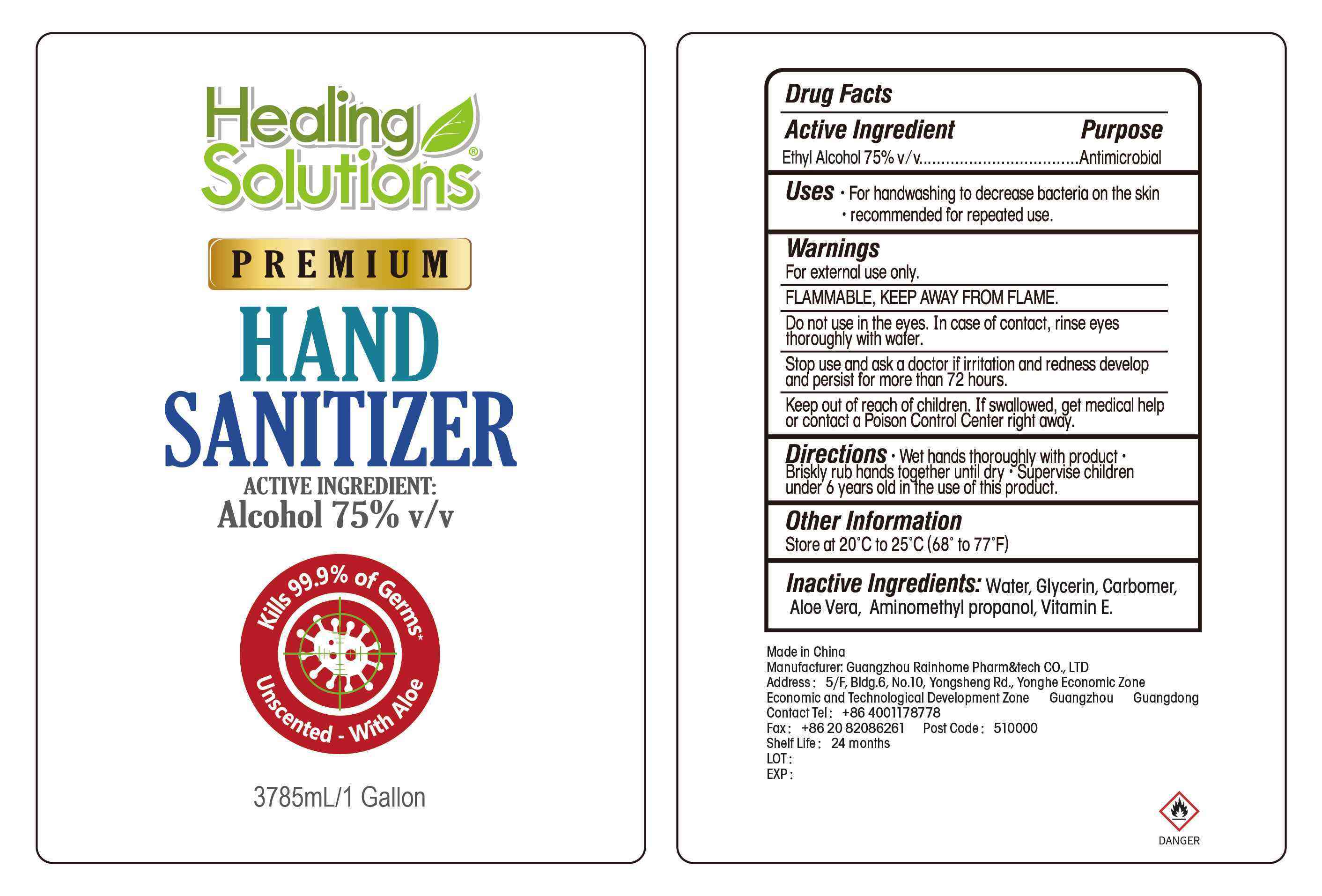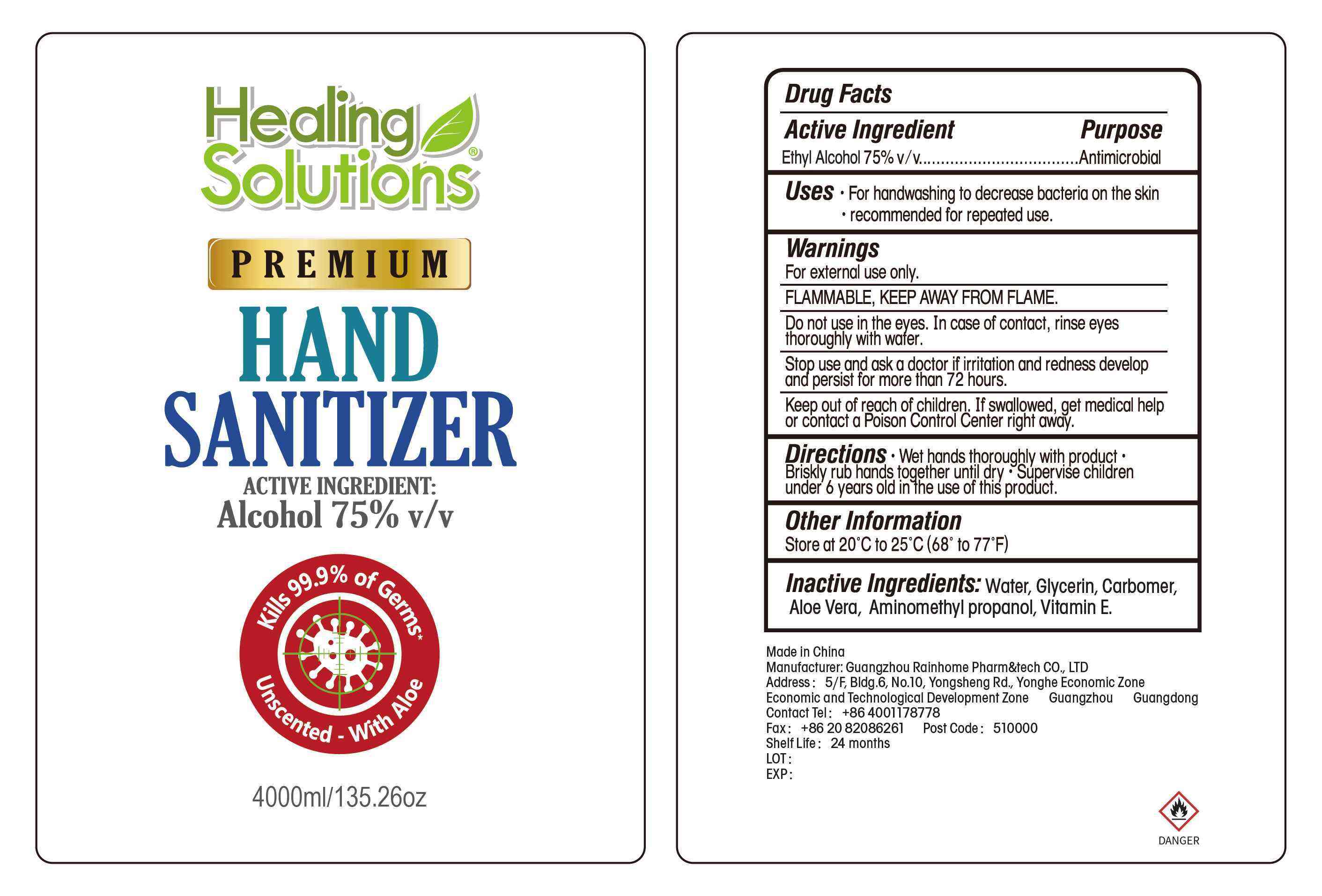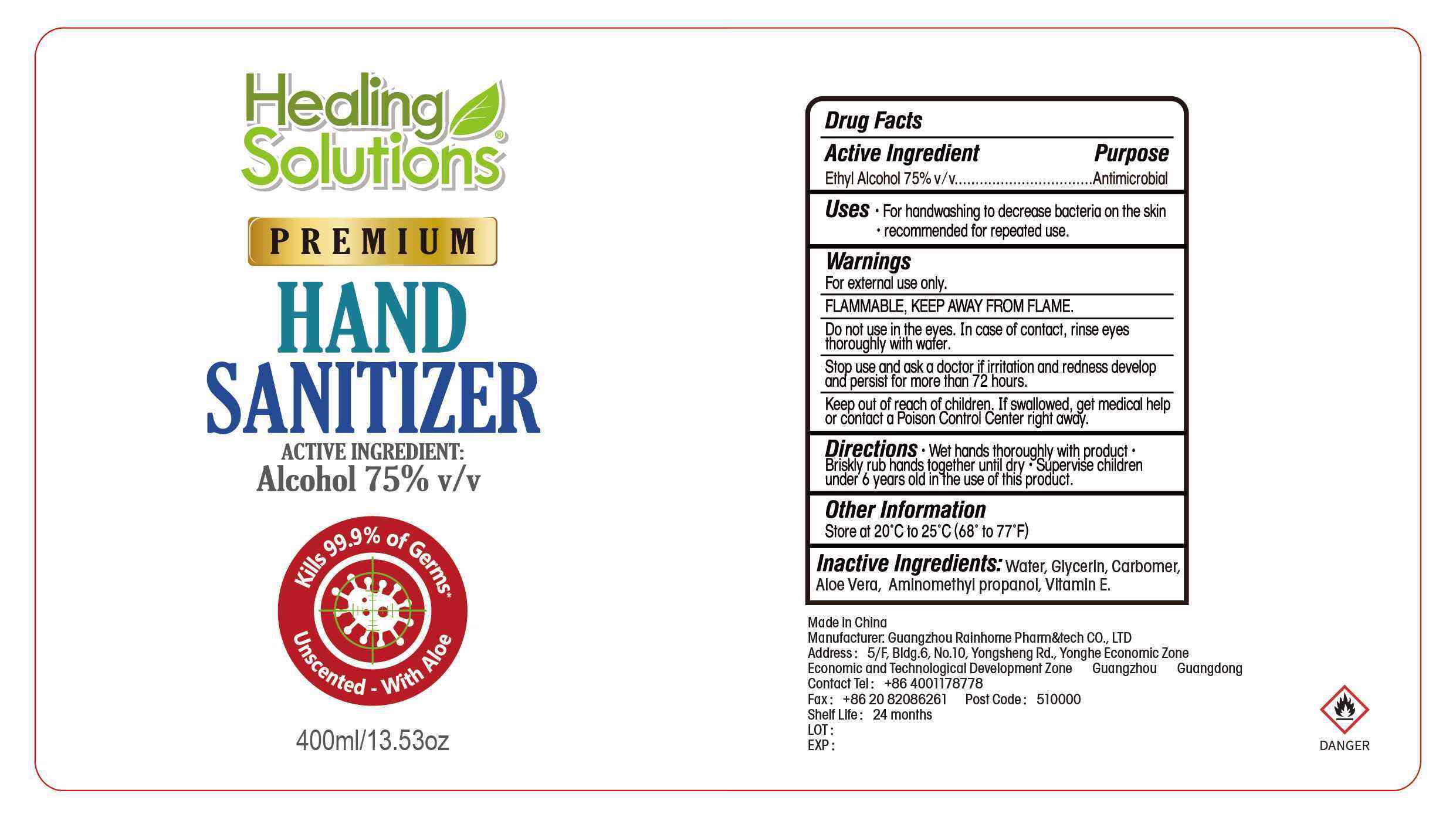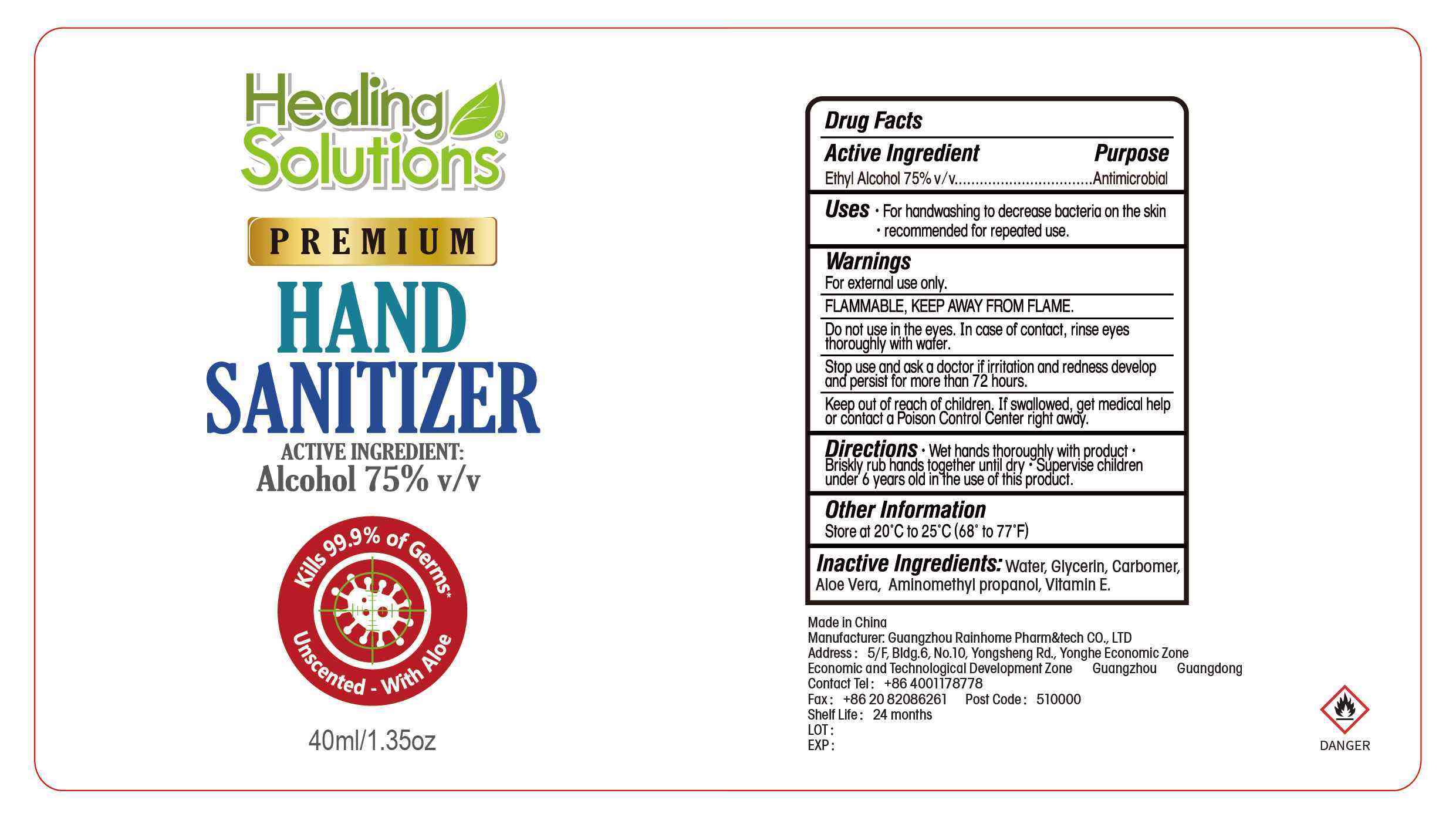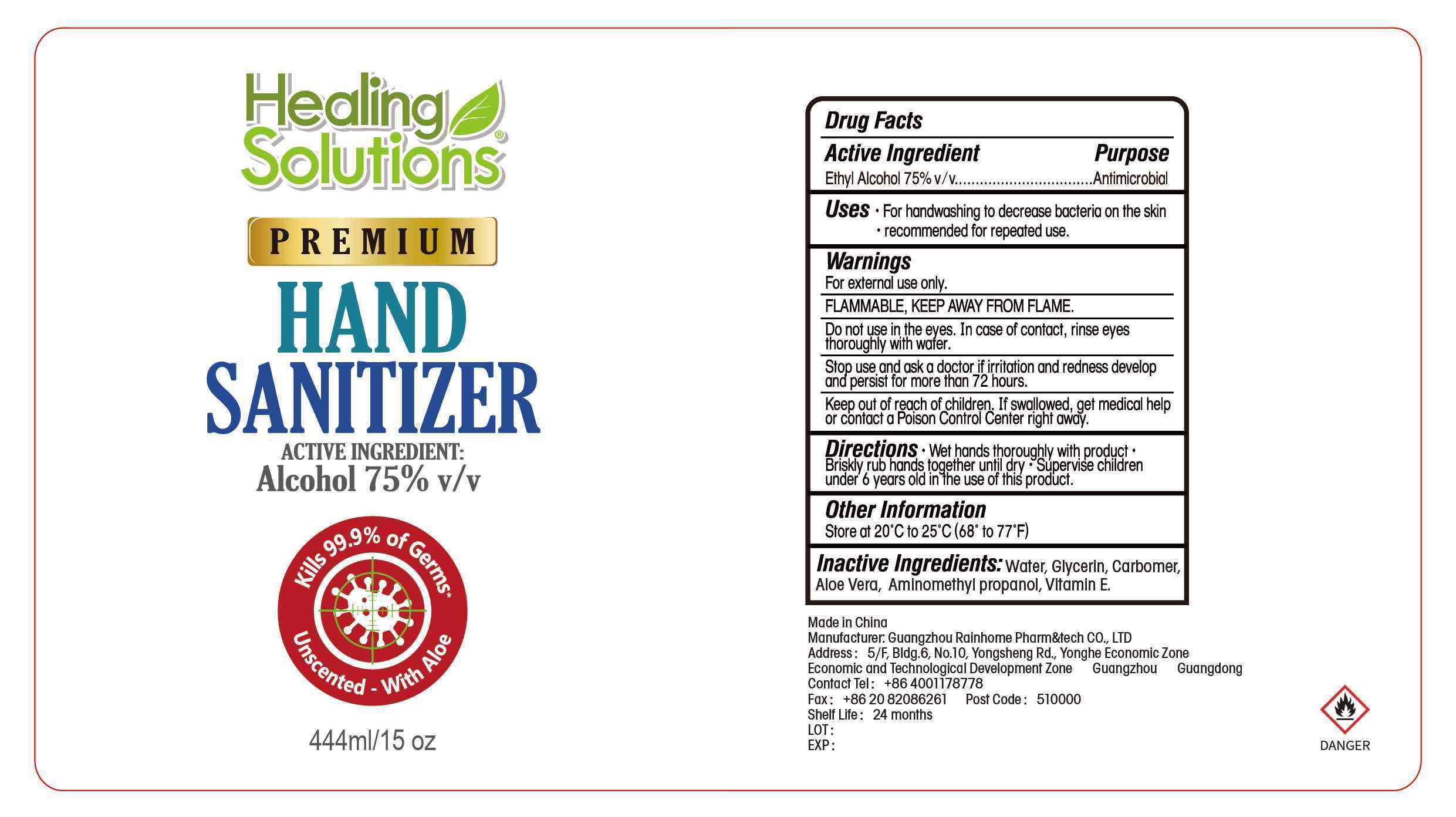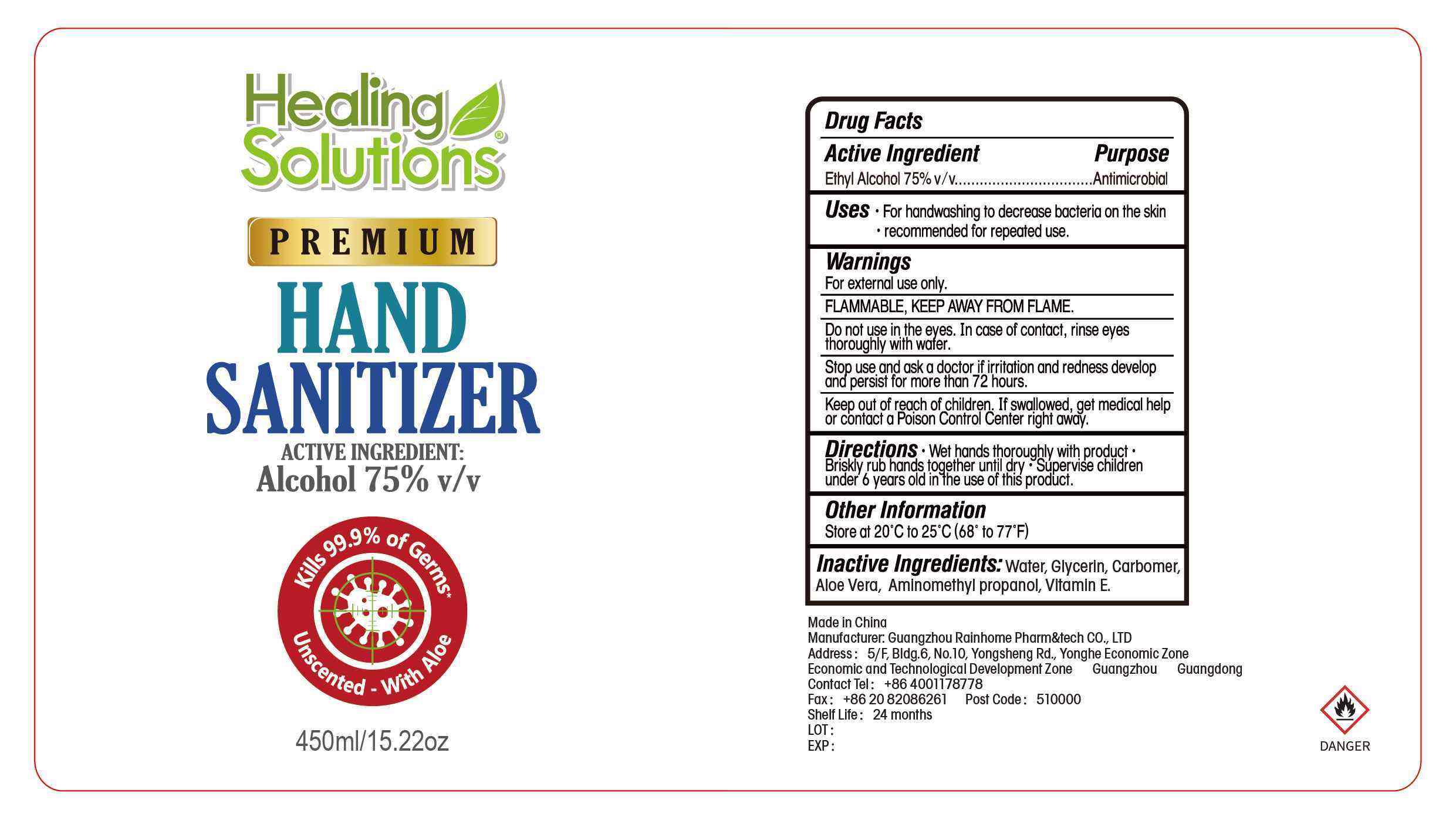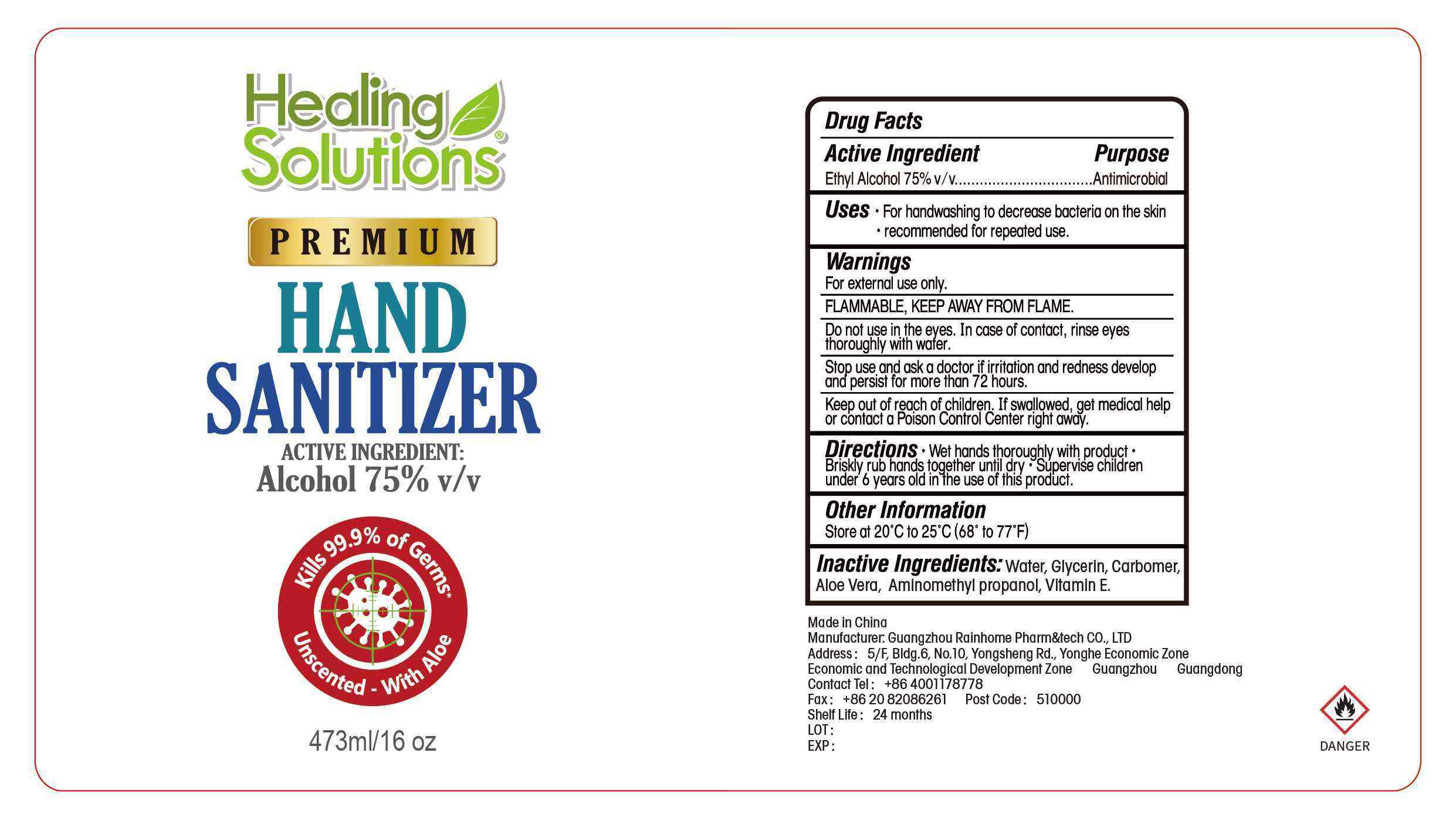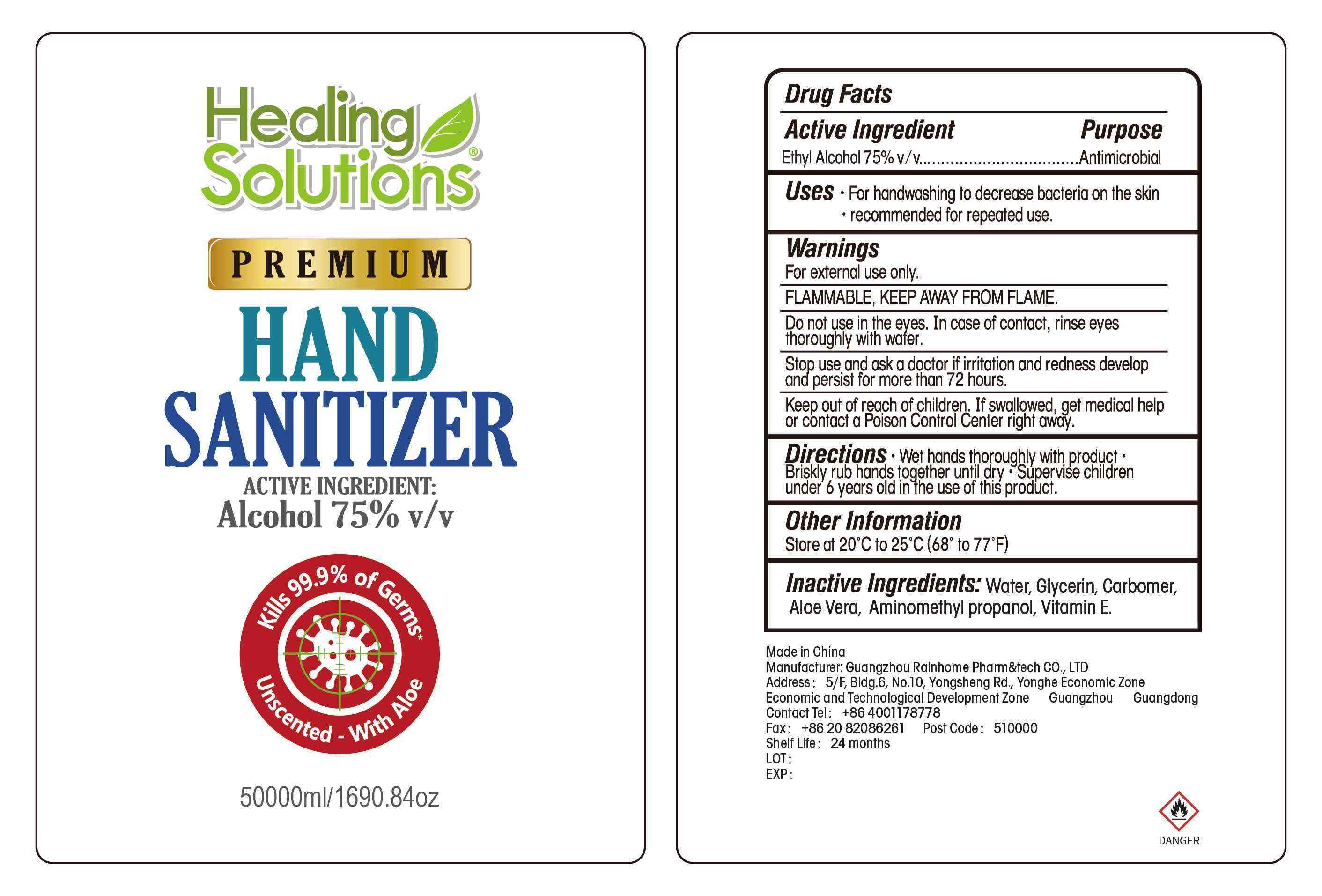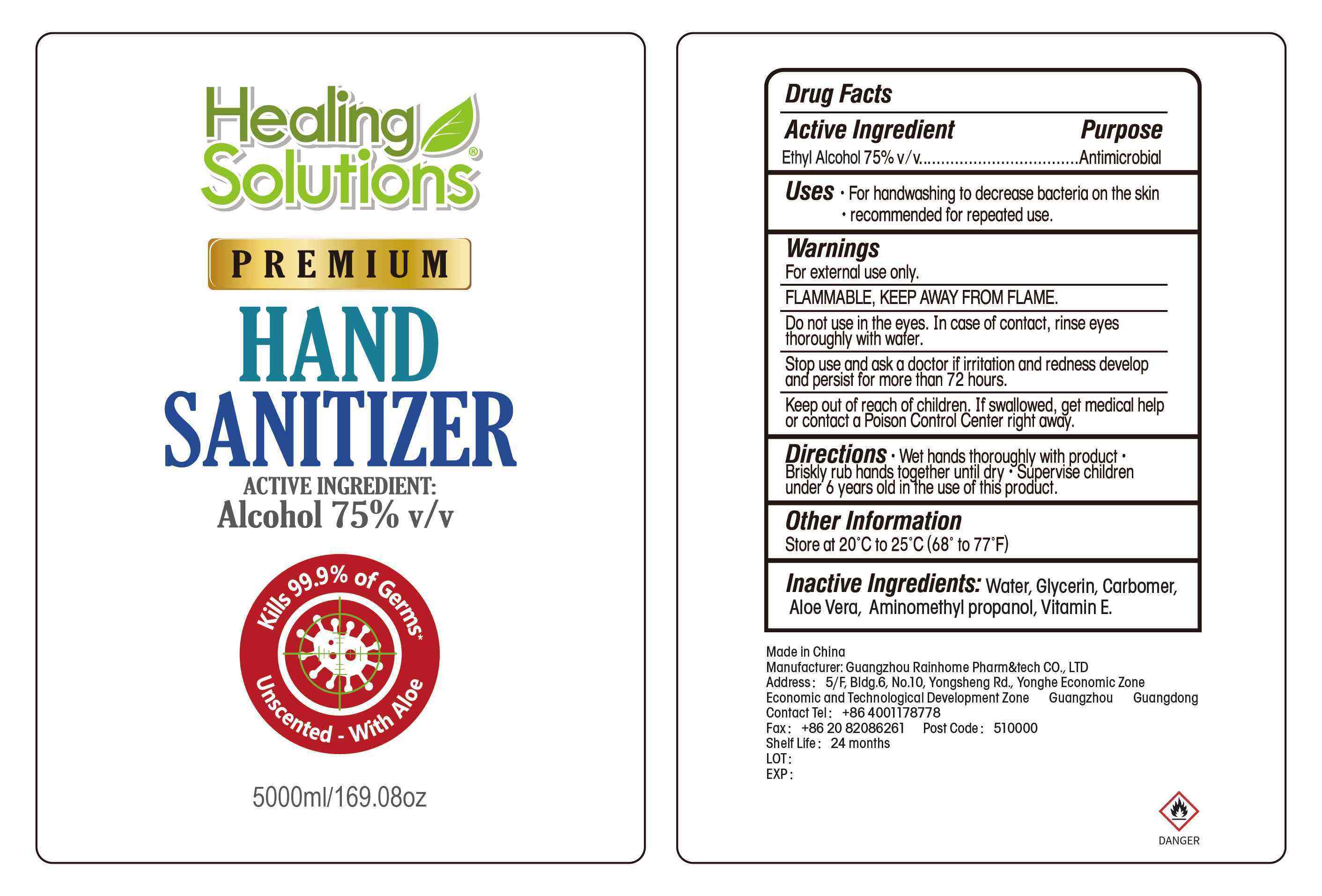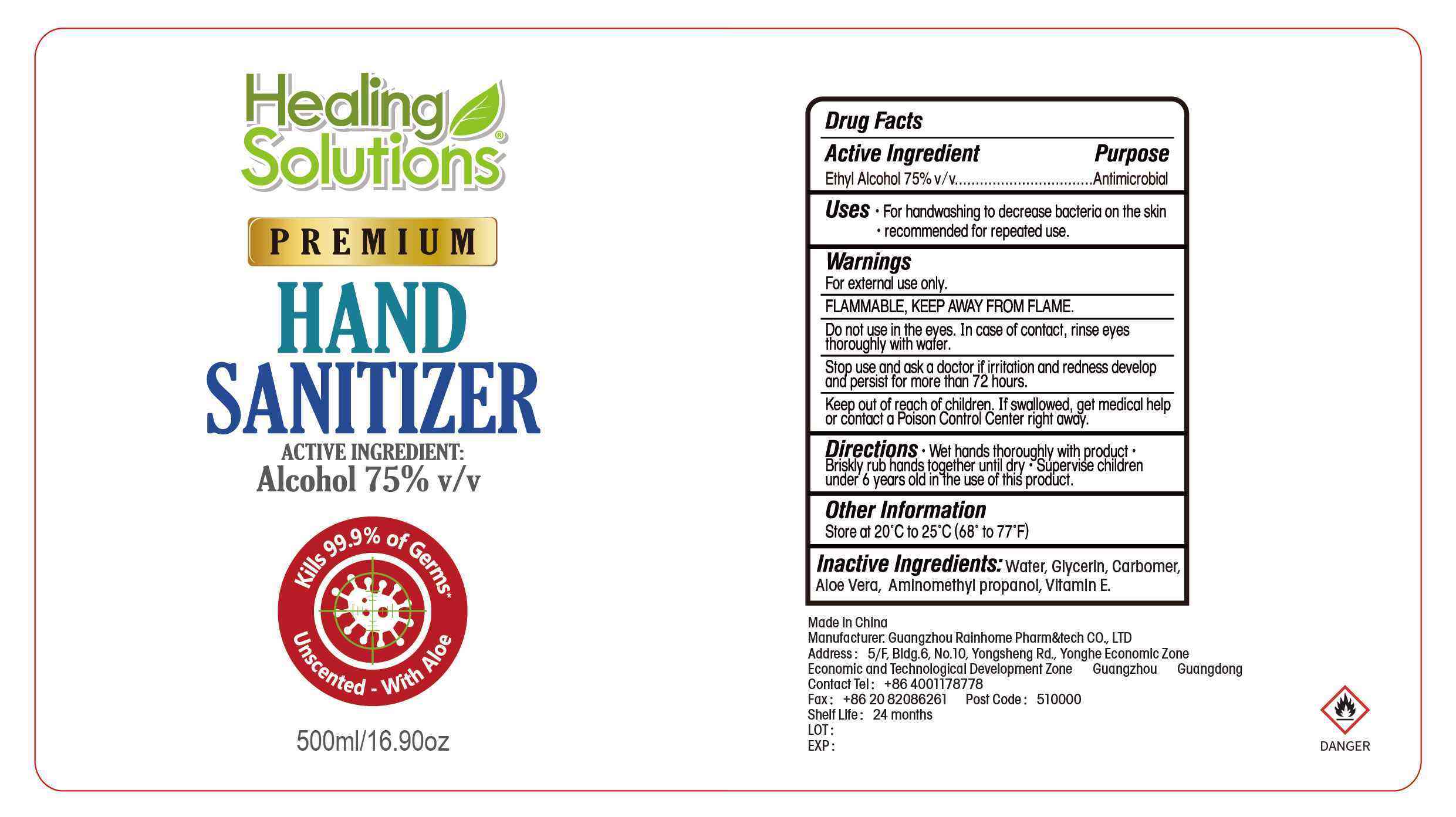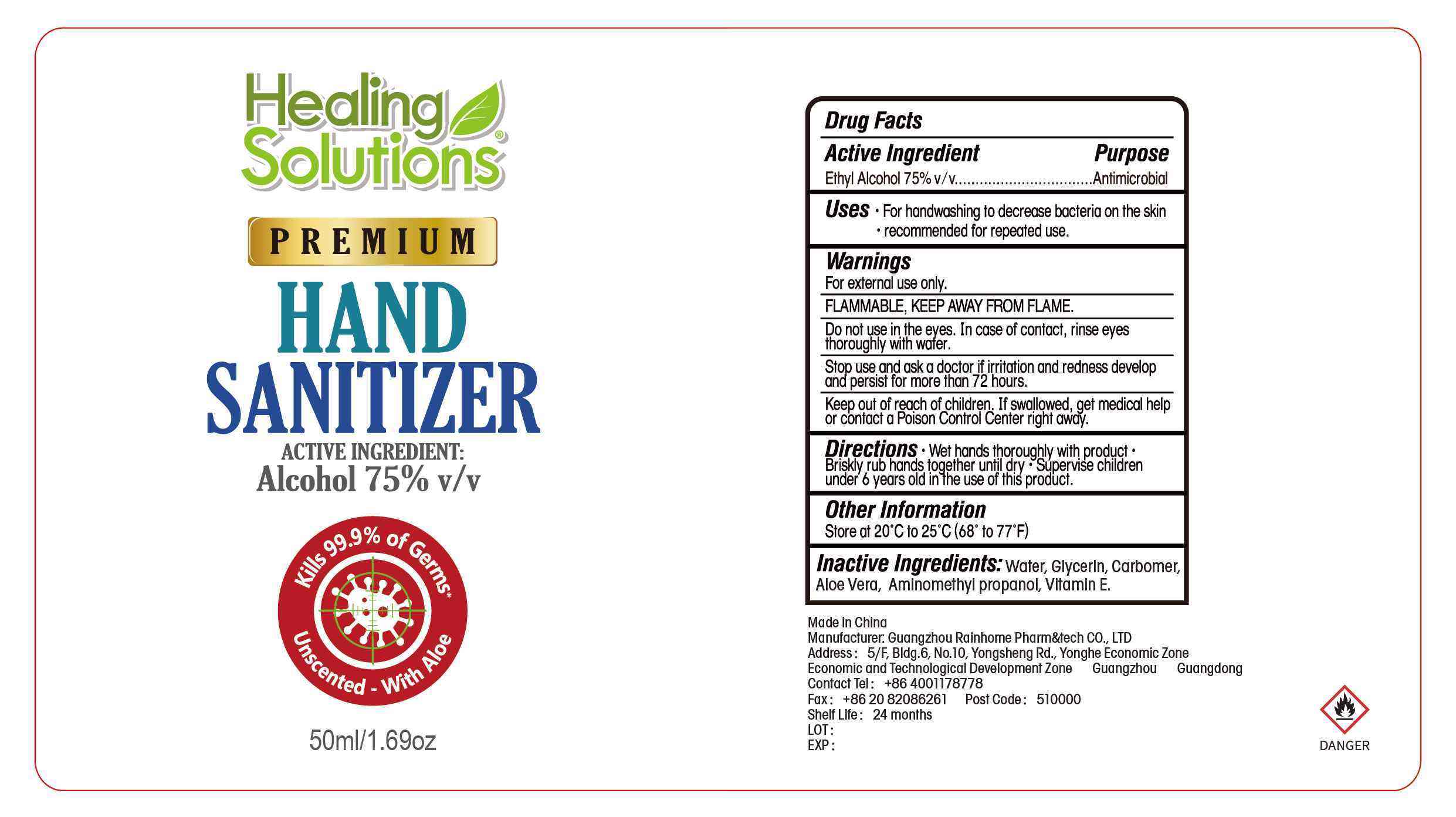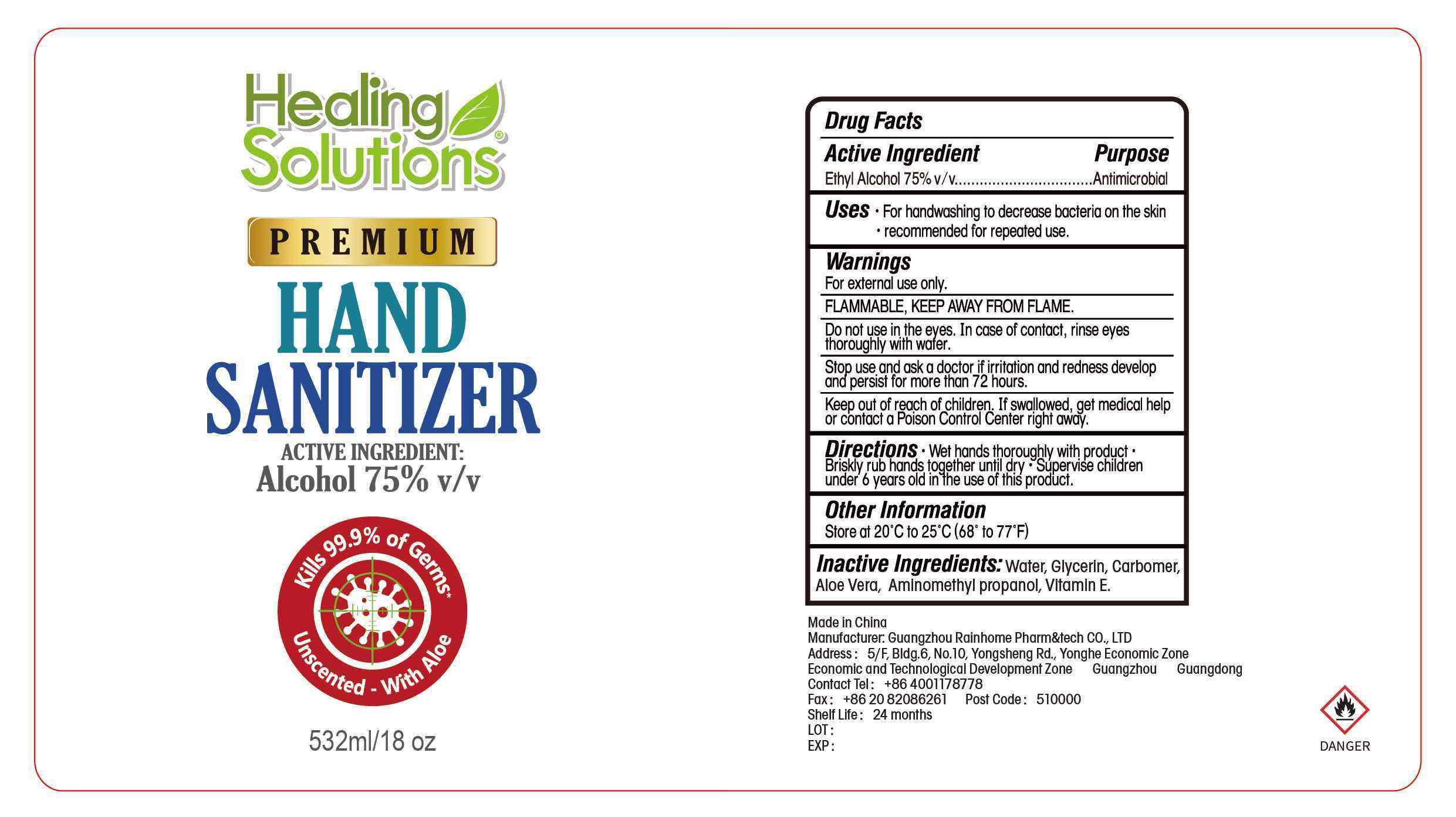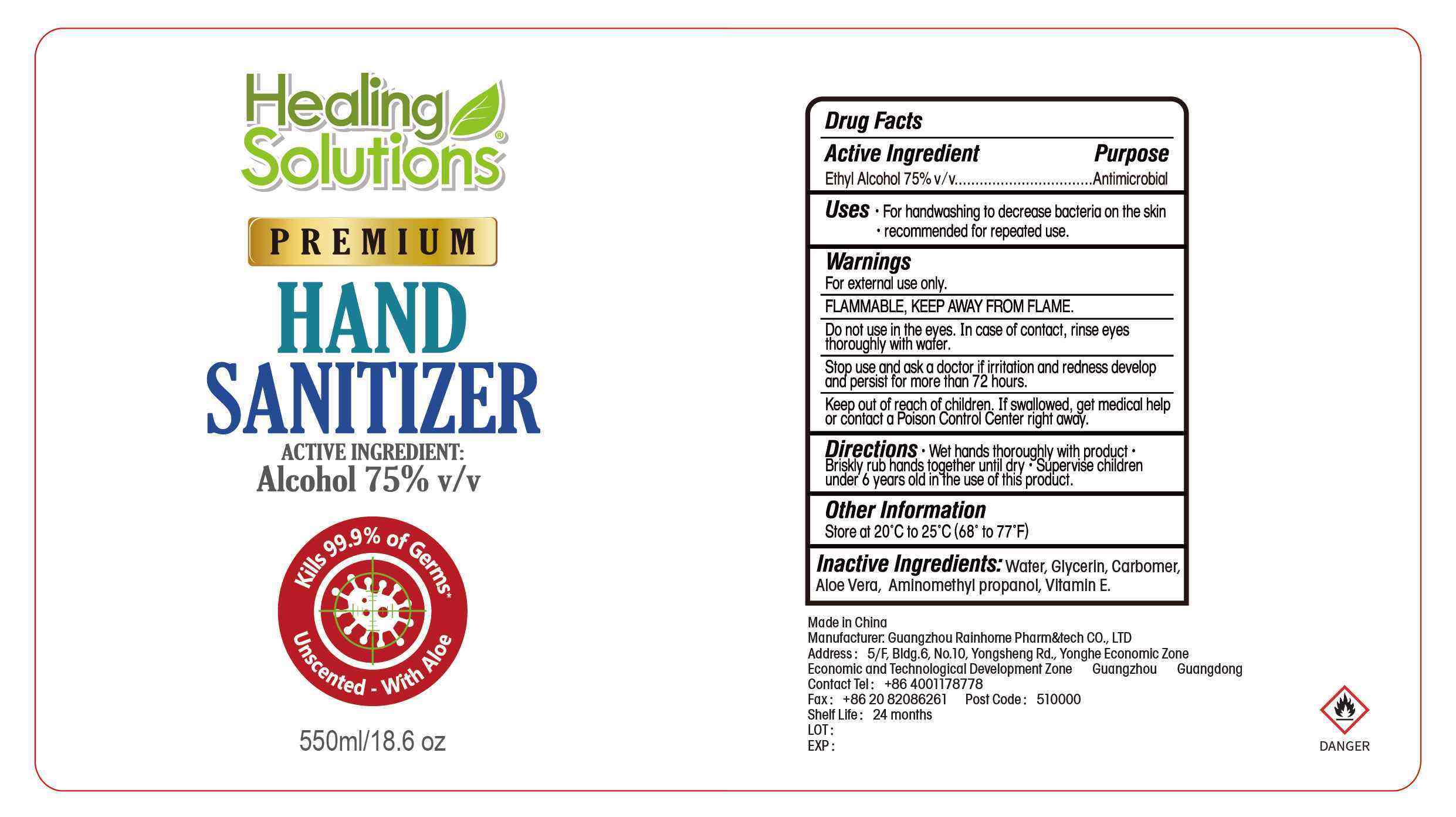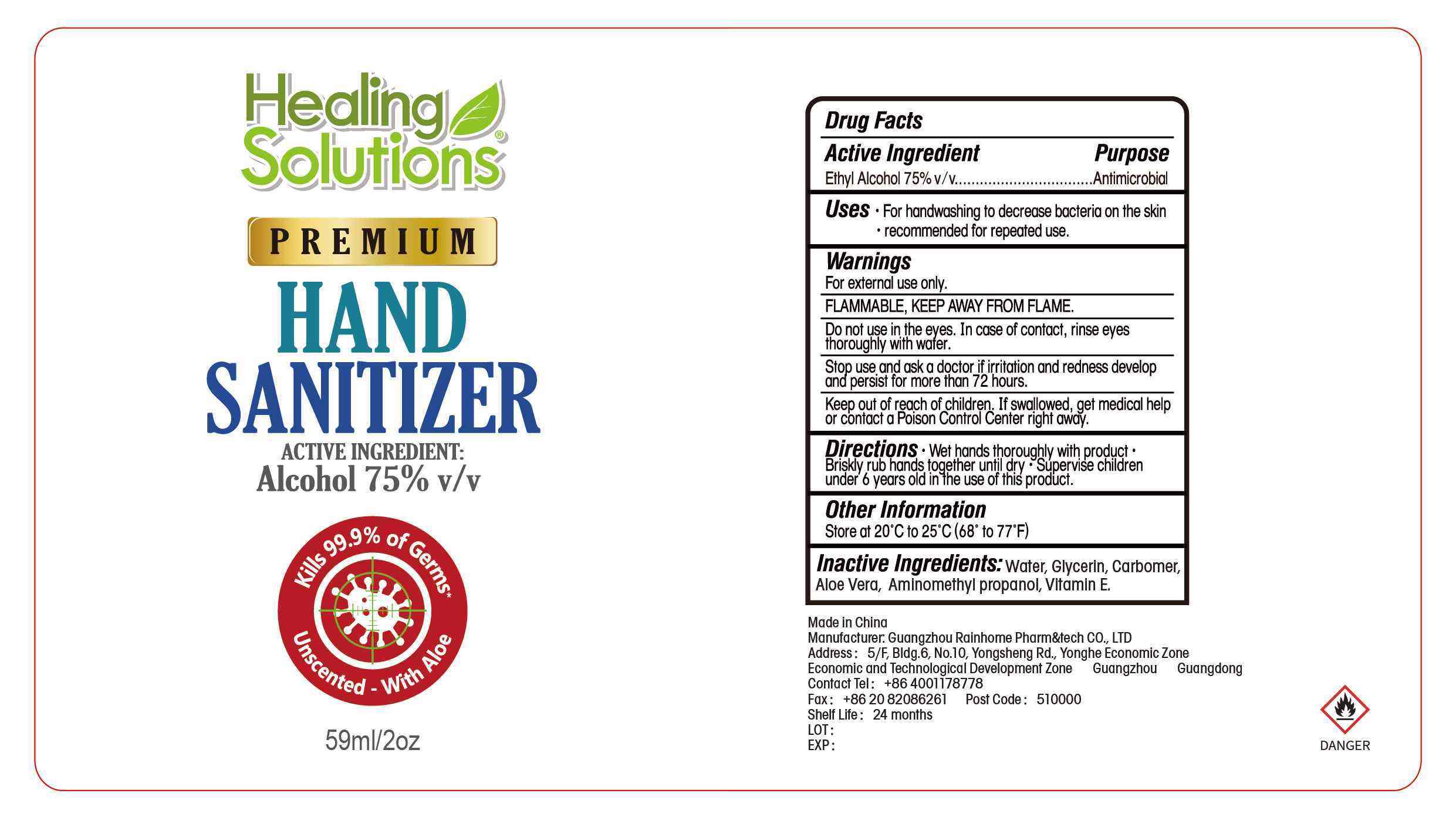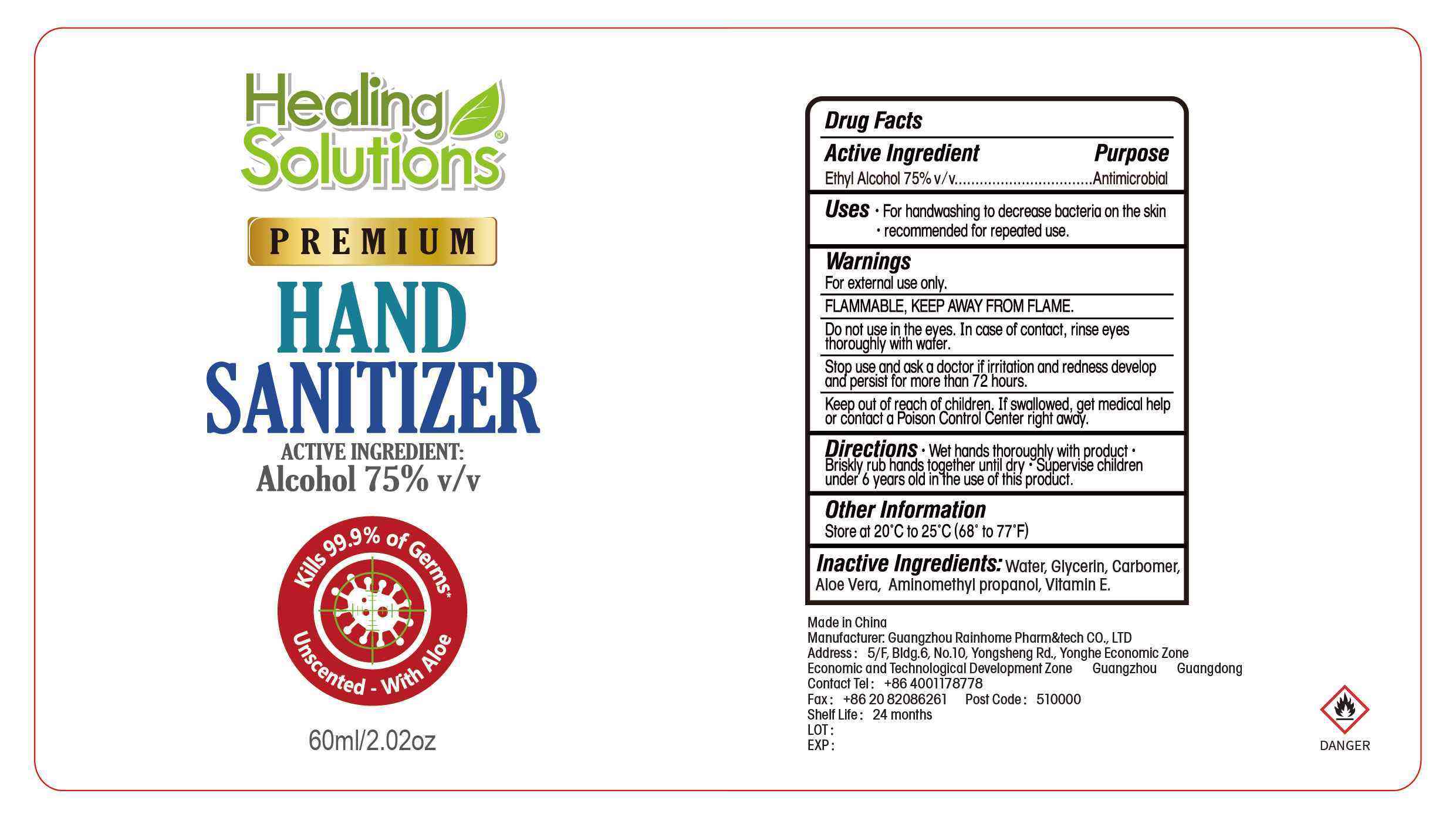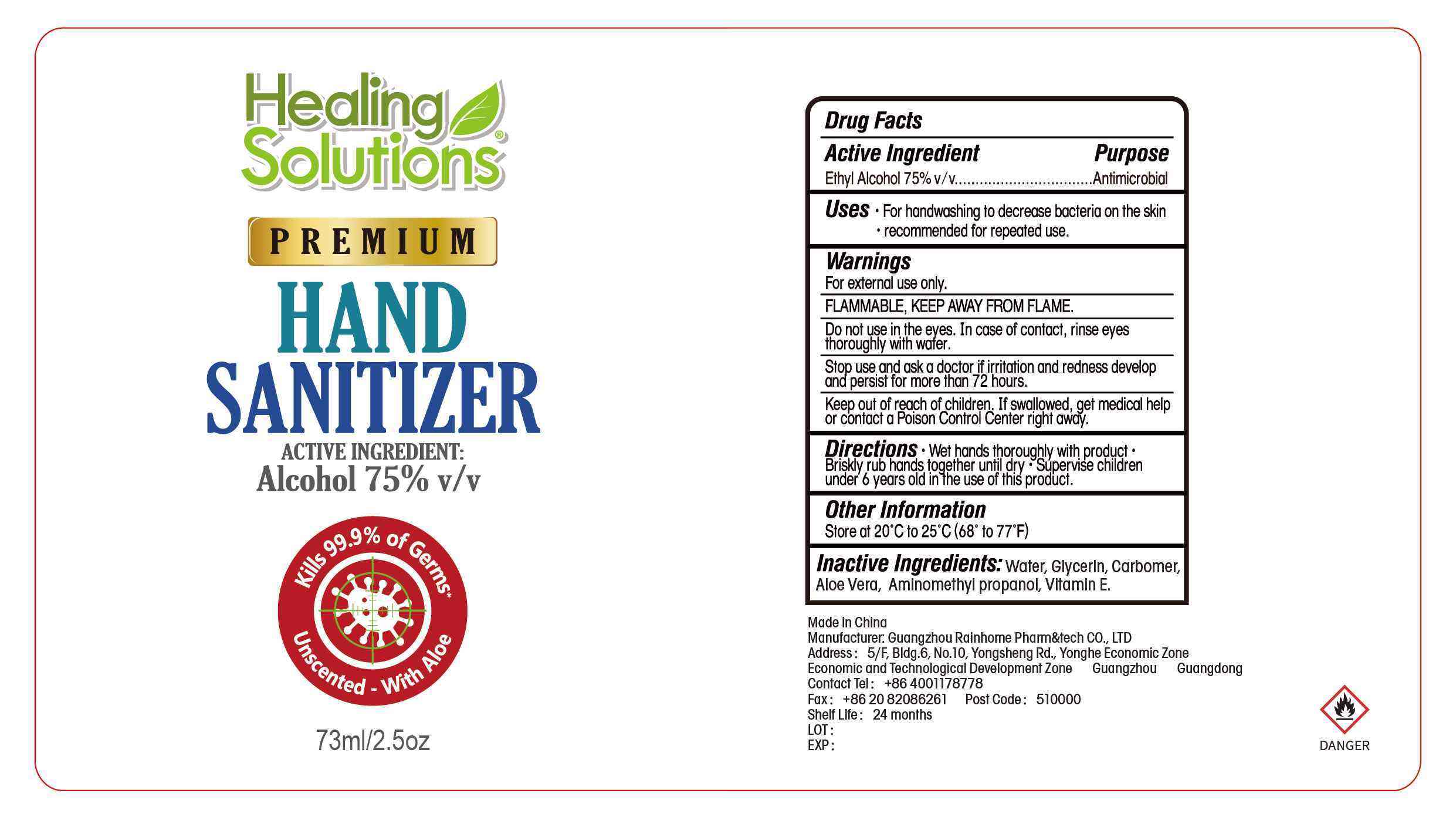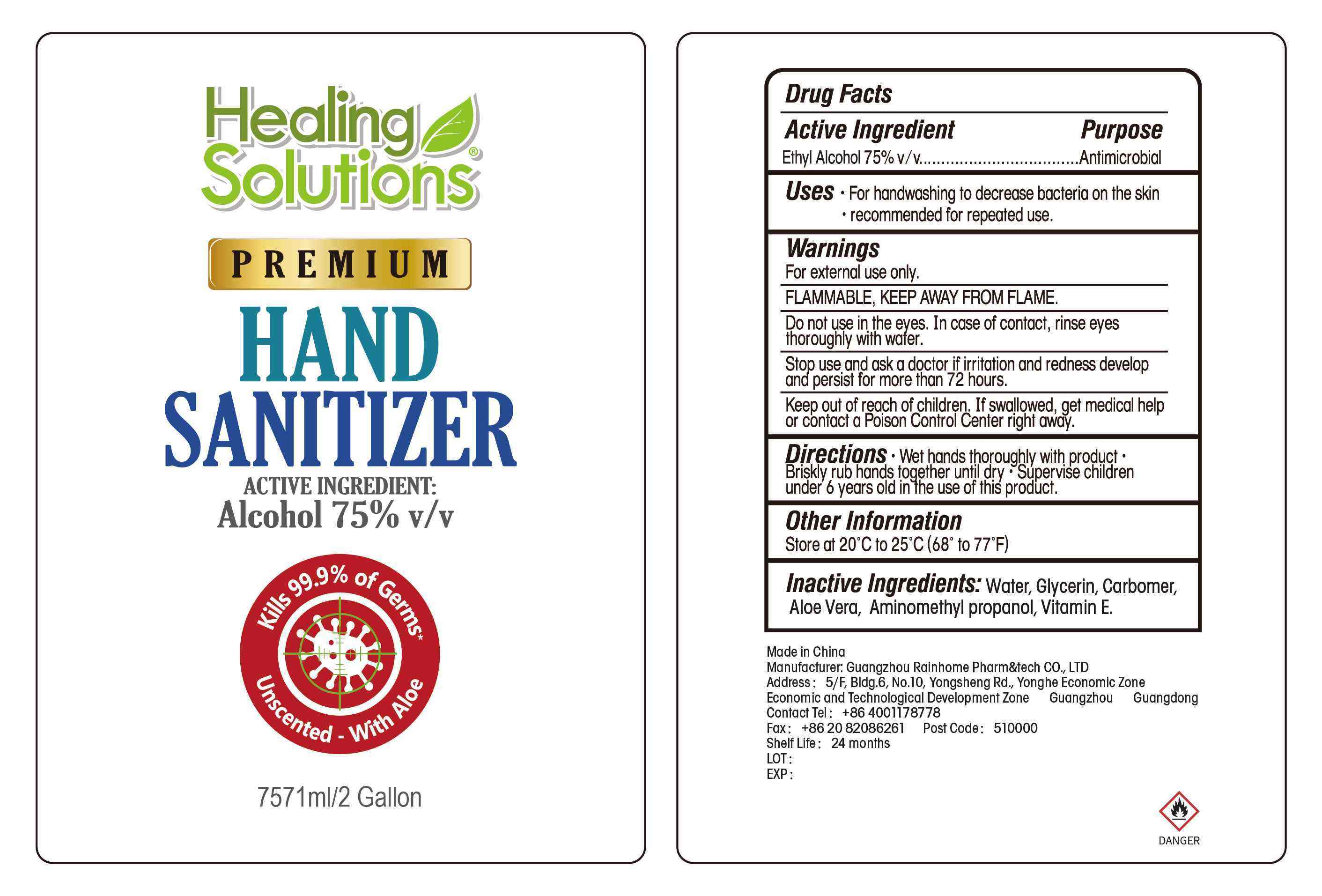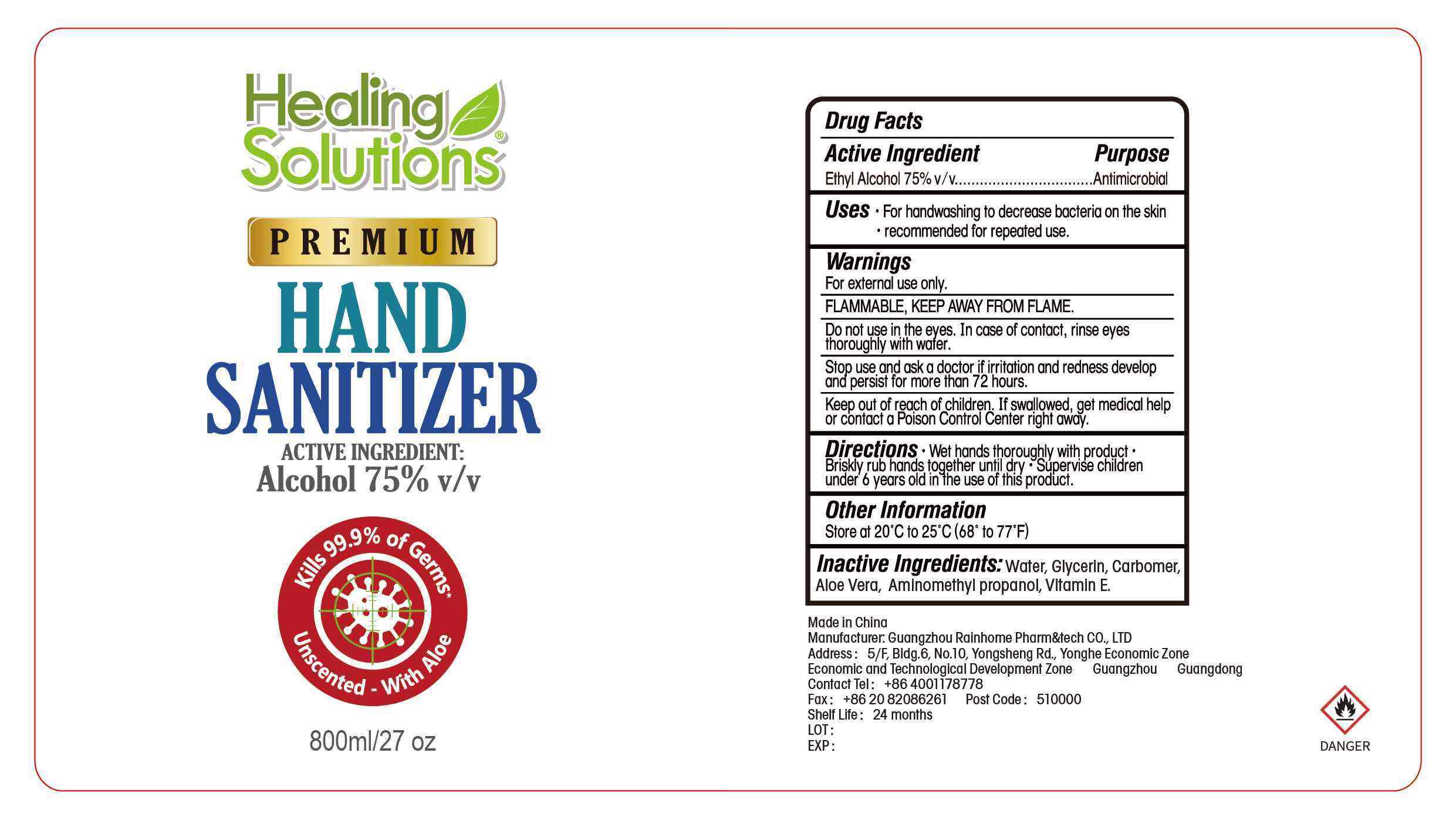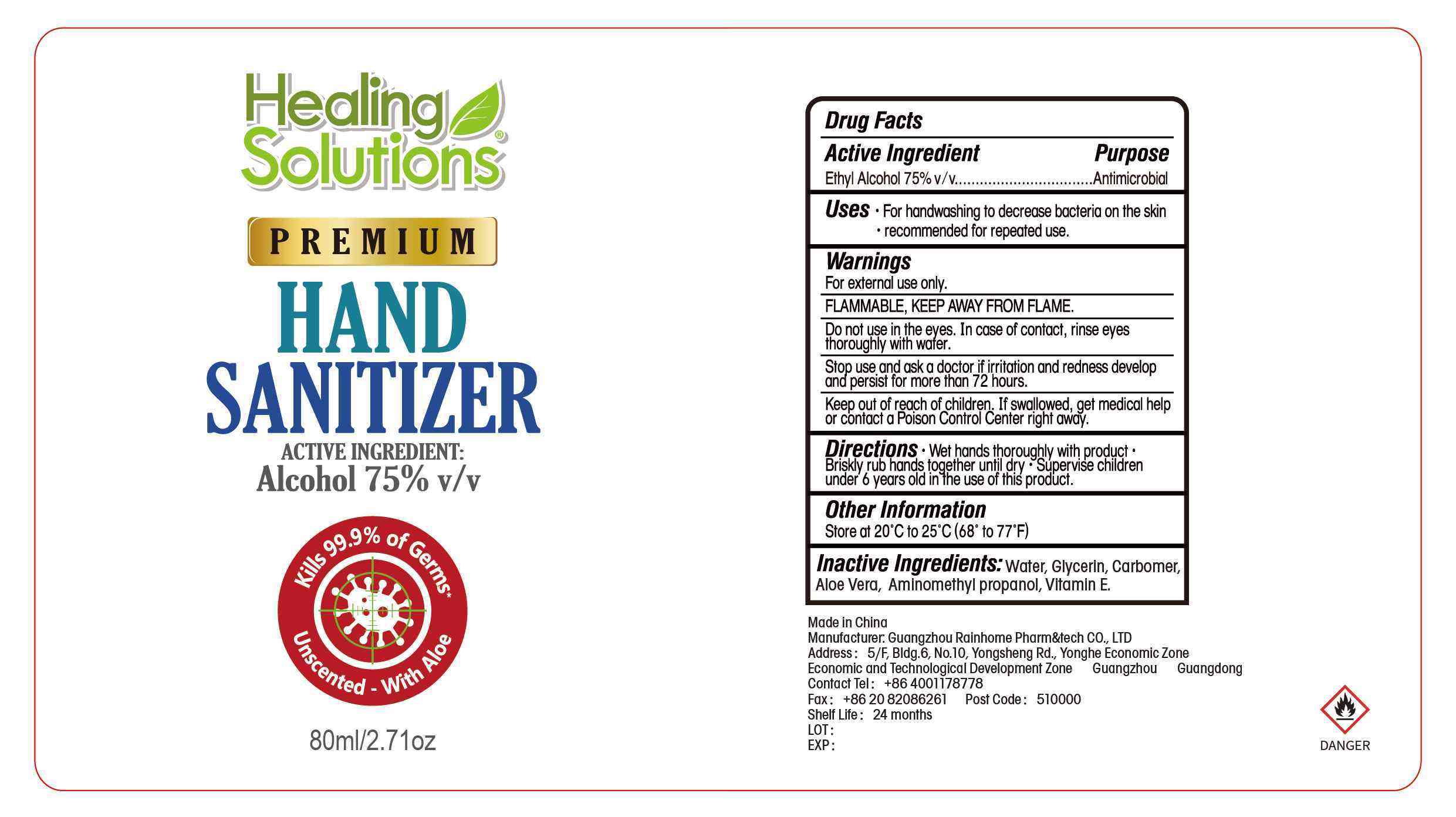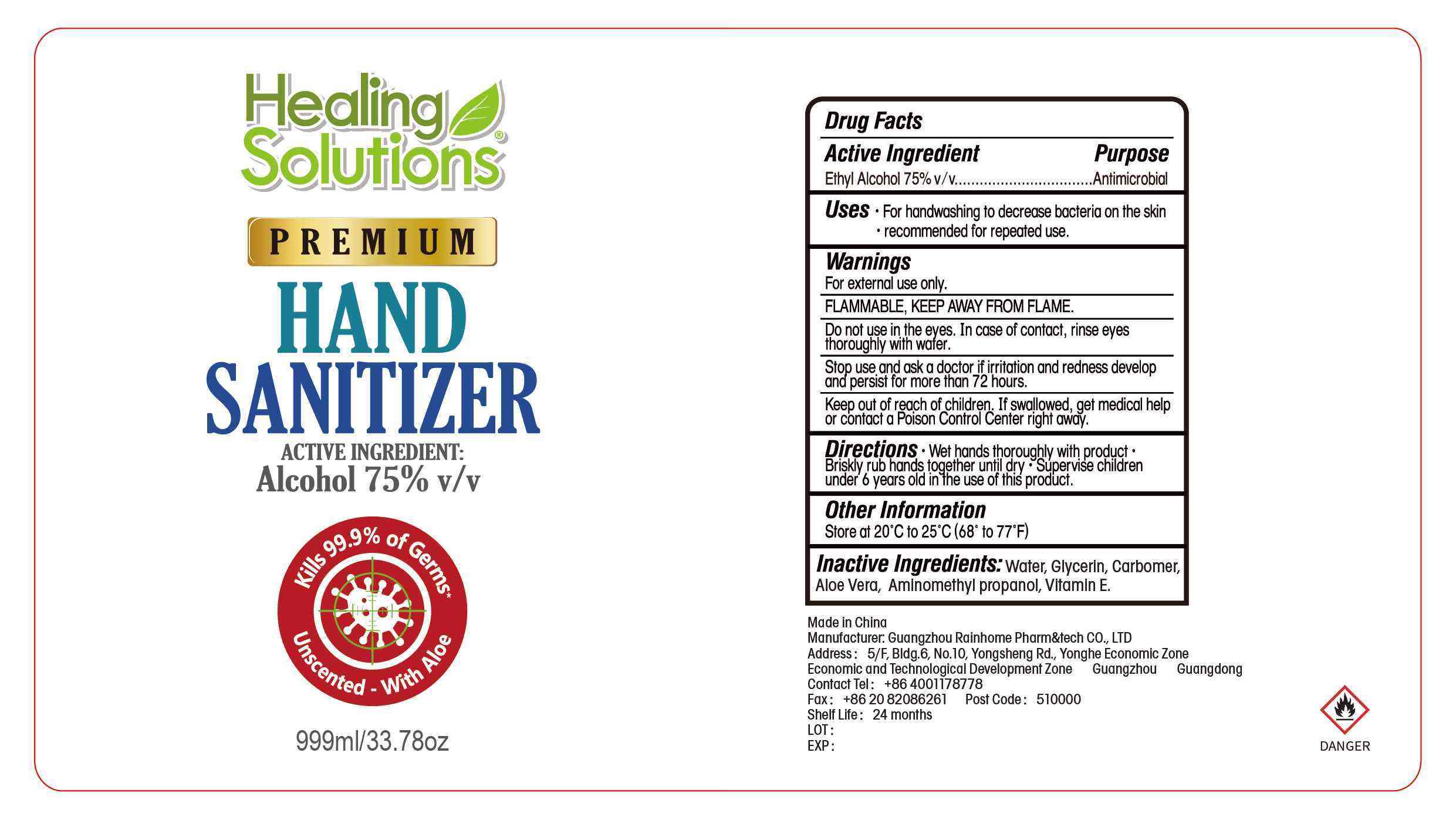 DRUG LABEL: Hand Sanitizer
NDC: 78126-008 | Form: GEL
Manufacturer: GUANGZHOU RAINHOME PHARM&TECH CO., LTD
Category: otc | Type: HUMAN OTC DRUG LABEL
Date: 20200515

ACTIVE INGREDIENTS: ALCOHOL 75 mL/100 mL
INACTIVE INGREDIENTS: GLYCERIN; CARBOMER COPOLYMER TYPE A (ALLYL PENTAERYTHRITOL CROSSLINKED); WATER; AMINOMETHYLPROPANOL; ALOE VERA LEAF; .ALPHA.-TOCOPHEROL ACETATE

Hand Sanitizer

Active Ingredient(s)

Ethyl Alcohol 75% v/v.

Purpose

Antimicrobial.

Use

For handwashing to decrease bacteria on the skin.
recommended for repeated use.

Warnings

For external use only.
FLAMMABLE. KEEP AWAY FROM FLAME.
Do not use in the eyes. In case of contact, rinse eyes thoroughly with wafer.
Stop use, and ask a doctor_ if irritation and redness developand persist for more than 72 hours.
Keep out of reach of children. If swallowed, get medical helpor contact a Poison Control Center right away.

Do not use in the eyes.

Stop use and ask a doctor if irritation or rash occurs. These may be signs of a serious condition.
Keep out of reach of children. If swallowed, get medical help or contact a Poison Control Center right away.

Stop use and ask a doctor if irritation and redness developand persist for more than 72 hours.

Keep out of reach of children. If swallowed, get medical help or contact a Poison Control Center right away.

Directions

Wet hands thoroughly with product.
Briskly rub hands together until dry.
Supervise childrenunder 6 years old in the use of this product.

Other information

Store at 20 C to 25C (68° to 77° F）

Inactive ingredients

Water, GlycerIn, Carbomer,Aloe Vera, AmInomethyl propanol, Vitamin E